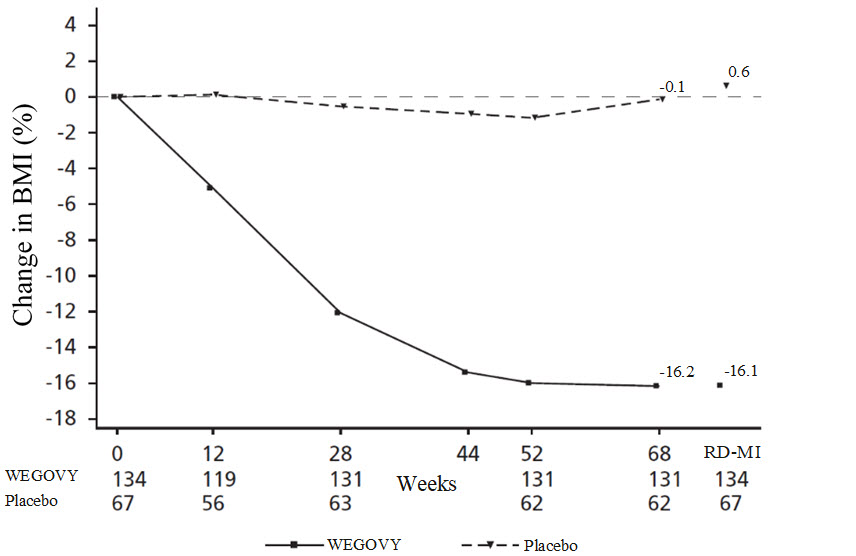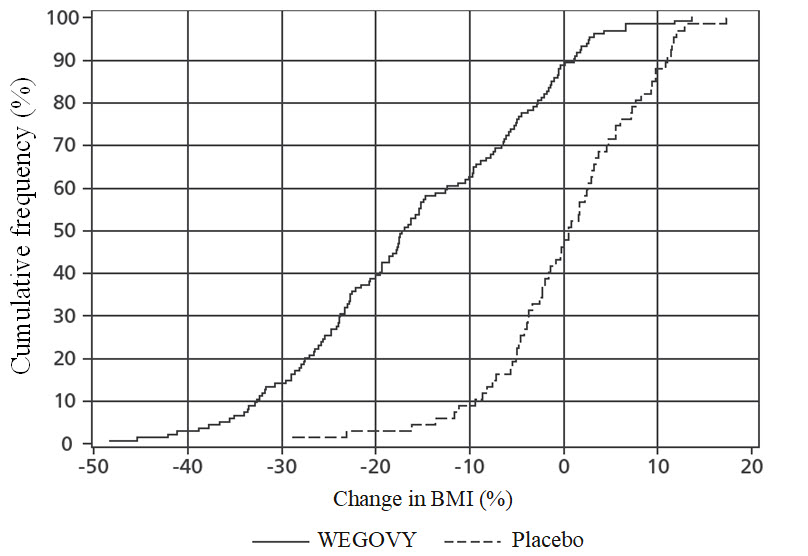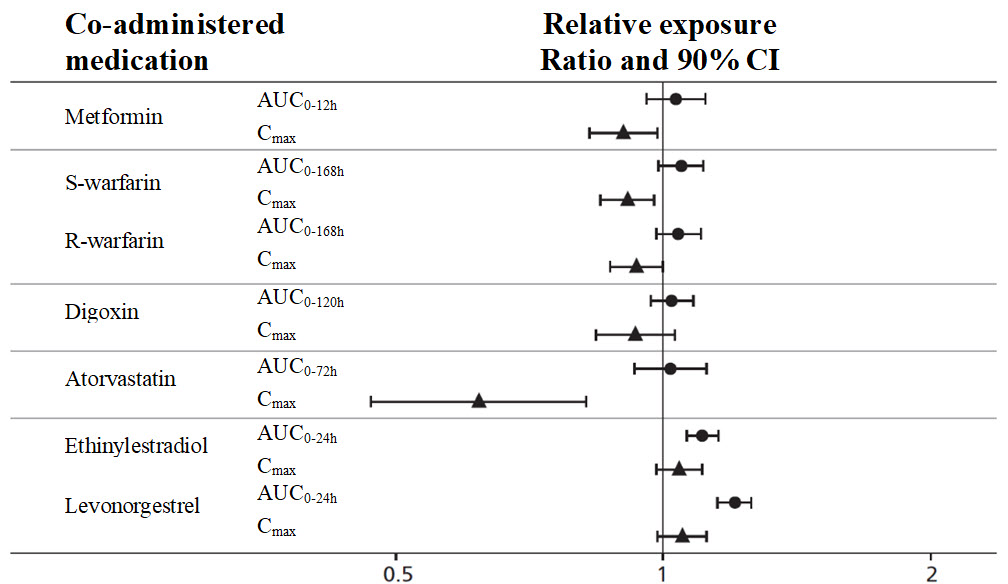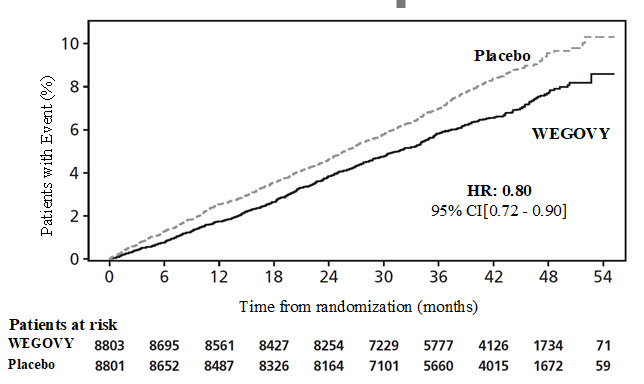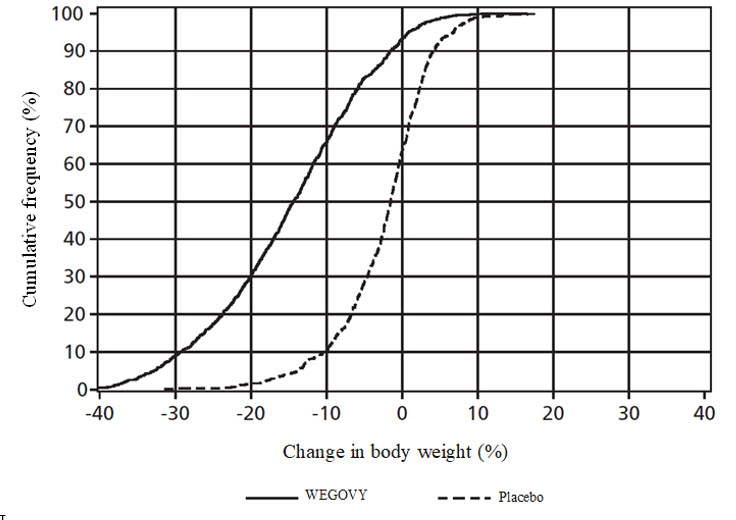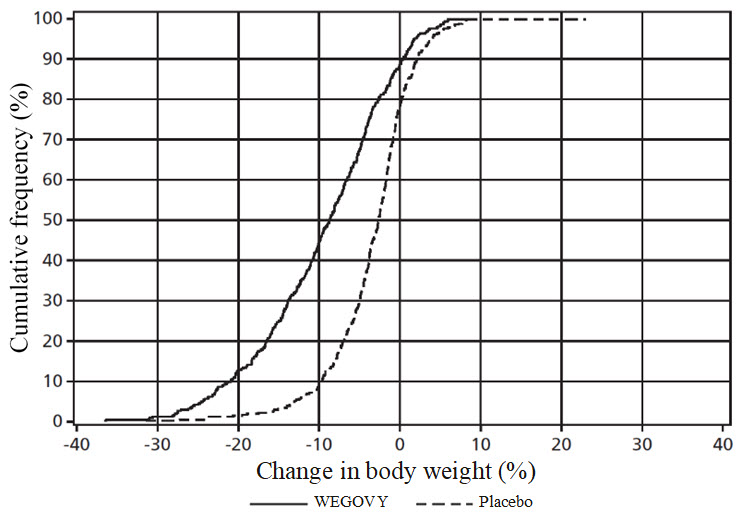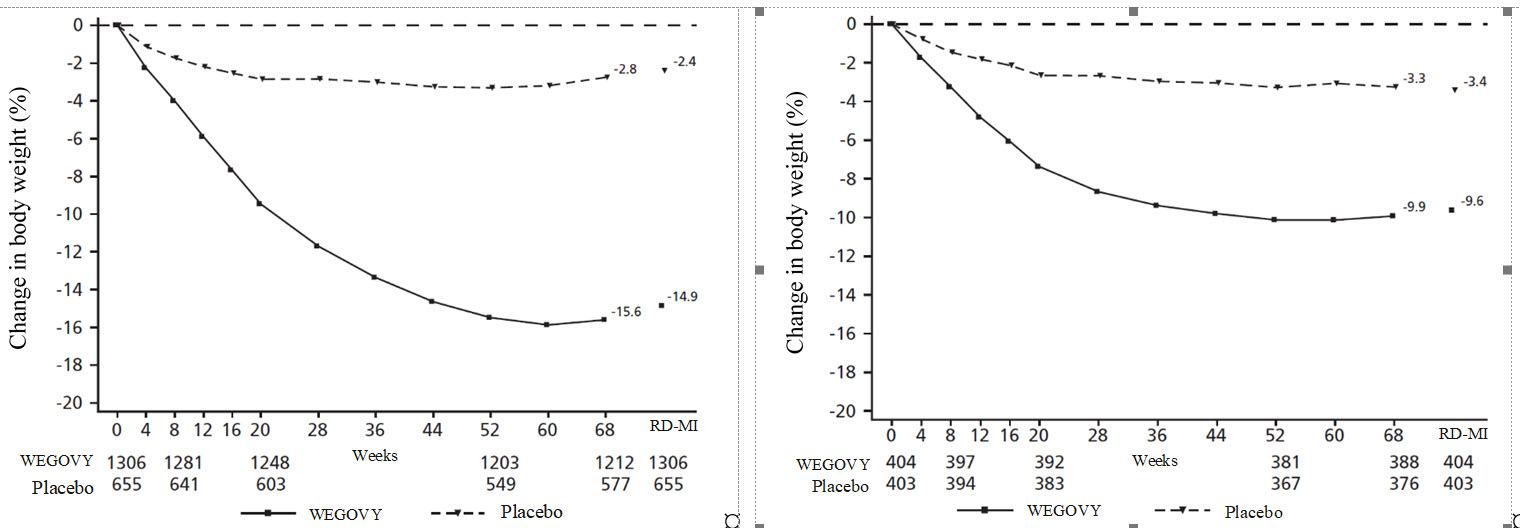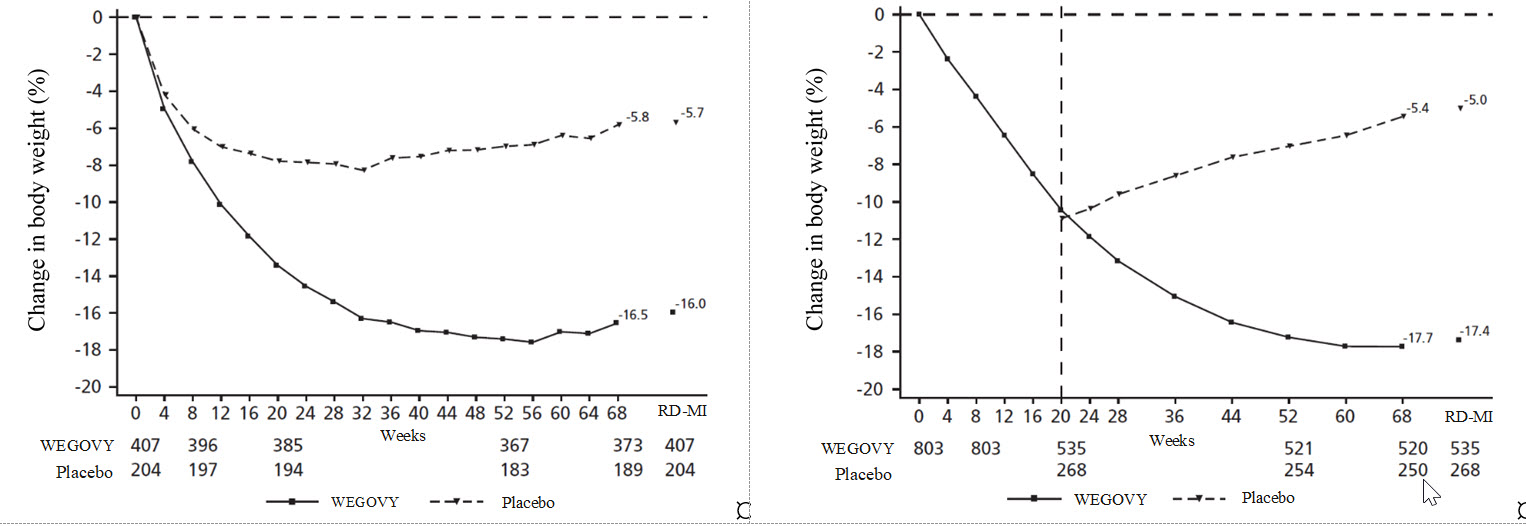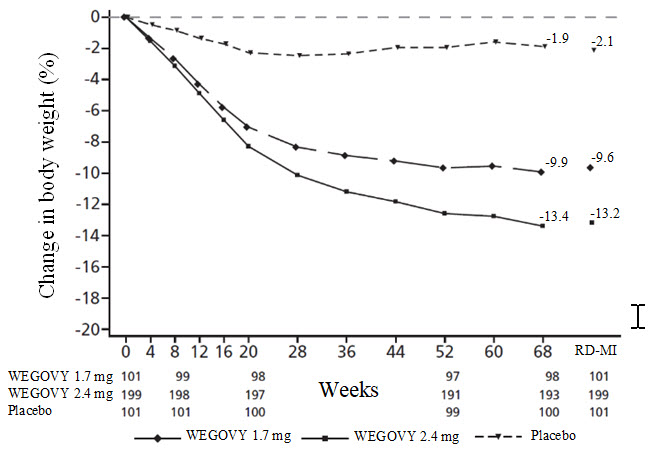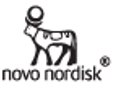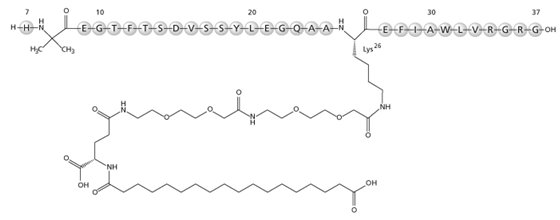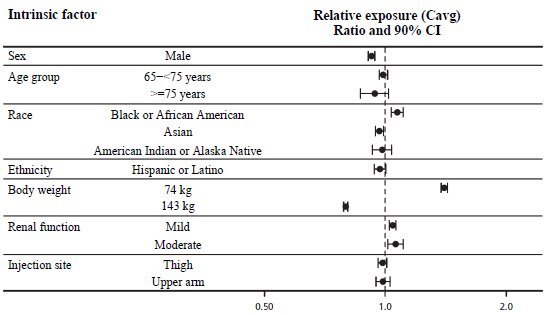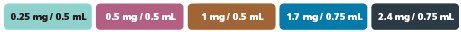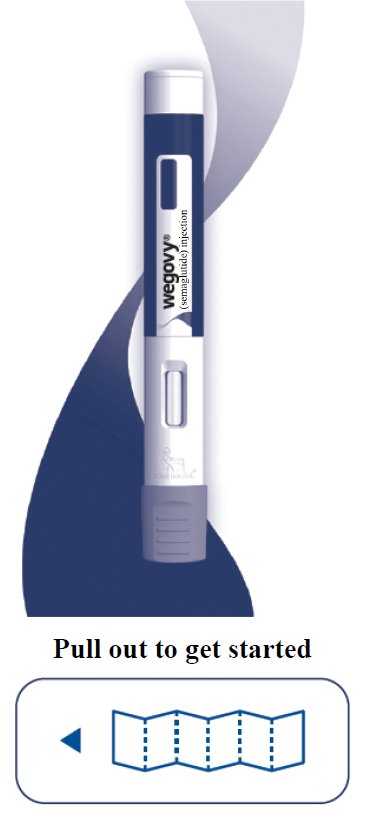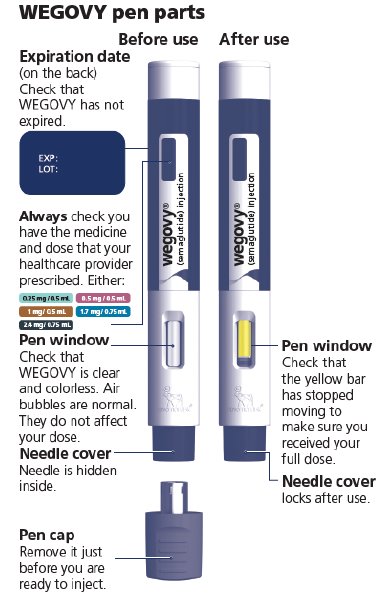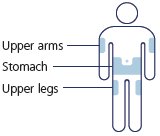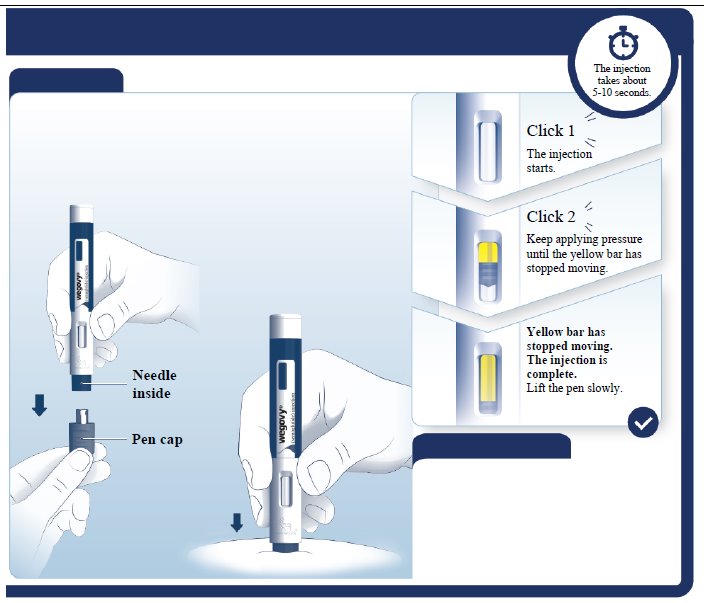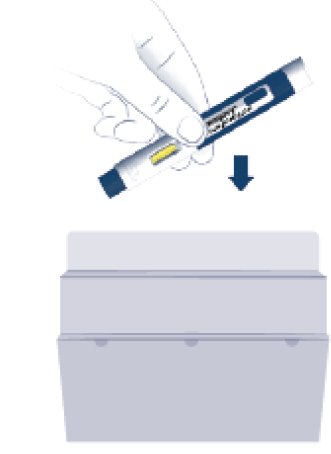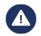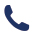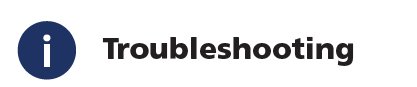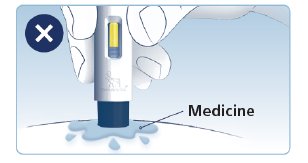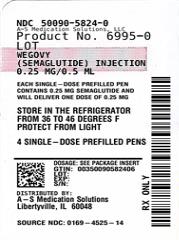 DRUG LABEL: WEGOVY
NDC: 50090-5824 | Form: INJECTION, SOLUTION
Manufacturer: A-S Medication Solutions
Category: prescription | Type: HUMAN PRESCRIPTION DRUG LABEL
Date: 20240423

ACTIVE INGREDIENTS: SEMAGLUTIDE 0.25 mg/0.5 mL
INACTIVE INGREDIENTS: SODIUM PHOSPHATE, DIBASIC, DIHYDRATE; SODIUM CHLORIDE; WATER

HIGHLIGHTS OF PRESCRIBING INFORMATION

These highlights do not include all the information needed to use WEGOVY safely and effectively. See full prescribing information for WEGOVY.
WEGOVY (semaglutide) injection, for subcutaneous use
Initial U.S. Approval: 2017

RECENT MAJOR CHANGES

Indications and Usage (1)………………………………….03/2024

Dosing and Administration (2.2)…………………………. 07/2023

Warnings and Precautions, Hypoglycemia (5.4)…………..03/2024

WARNING: RISK OF THYROID C-CELL TUMORS

See full prescribing information for complete boxed warning.

- In rodents, semaglutide causes thyroid C-cell tumors at clinically relevant exposures. It is unknown whether WEGOVY causes thyroid C-cell tumors, including medullary thyroid carcinoma (MTC), in humans as the human relevance of semaglutide-induced rodent thyroid C-cell tumors has not been determined (5.1, 13.1).
- WEGOVY is contraindicated in patients with a personal or family history of MTC or in patients with Multiple Endocrine Neoplasia syndrome type 2 (MEN 2). Counsel patients regarding the potential risk of MTC and symptoms of thyroid tumors (4, 5.1).

1 INDICATIONS AND USAGE

WEGOVY is a glucagon-like peptide-1 (GLP-1) receptor agonist indicated in combination with a reduced calorie diet and increased physical activity:

- to reduce the risk of major adverse cardiovascular events (cardiovascular death, non-fatal myocardial infarction, or non-fatal stroke) in adults with established cardiovascular disease and either obesity or overweight (1).
- to reduce excess body weight and maintain weight reduction long term in:
  - Adults and pediatric patients aged 12 years and older with obesity
  - Adults with overweight in the presence of at least one weight-related comorbid condition (1).

Limitations of Use:

  - Coadministration with other semaglutide-containing products or with any other GLP-1 receptor agonist is not recommended (1).

2 DOSAGE AND ADMINISTRATION

- Administer WEGOVY once weekly as an adjunct to diet and increased physical activity, on the same day each week, at any time of day, with or without meals (2.1).
  - Inject subcutaneously in the abdomen, thigh or upper arm (2.1).
- In patients with type 2 diabetes, monitor blood glucose prior to starting and during WEGOVY treatment (2.1).
- Initiate at 0.25 mg once weekly for 4 weeks. Then follow the dosage escalation schedule, titrating every 4 weeks to achieve the maintenance dosage (2.2, 2.3).
- The maintenance dosage of WEGOVY in adults is either 2.4 mg (recommended) or 1.7 mg once weekly (2.2).
- The maintenance dosage of WEGOVY in pediatric patients aged 12 years and older is 2.4 mg once weekly (2.3).

3 DOSAGE FORMS AND STRENGTHS

Injection: pre-filled, single-dose pen that delivers doses of 0.25 mg, 0.5 mg, 1 mg, 1.7 mg or 2.4 mg (3).

4 CONTRAINDICATIONS

- Personal or family history of MTC or in patients with MEN 2 (4).
- Known hypersensitivity to semaglutide or any of the excipients in WEGOVY (4).

5 WARNINGS AND PRECAUTIONS

- Acute Pancreatitis: Has occurred in clinical trials. Discontinue promptly if pancreatitis is suspected. Do not restart if pancreatitis is confirmed (5.2).
- Acute Gallbladder Disease: Has occurred in clinical trials. If cholelithiasis is suspected, gallbladder studies and clinical follow-up are indicated (5.3).
- Hypoglycemia: Concomitant use with insulin or an insulin secretagogue may increase the risk of hypoglycemia, including severe hypoglycemia. Reducing the dose of insulin or insulin secretagogue may be necessary. Inform all patients of the risk of hypoglycemia and educate them on the signs and symptoms of hypoglycemia (5.4).
- Acute Kidney Injury: Has occurred. Monitor renal function when initiating or escalating doses of WEGOVY in patients reporting severe adverse gastrointestinal reactions or in those with renal impairment reporting severe adverse gastrointestinal reactions (5.5).
- Hypersensitivity Reactions: Anaphylactic reactions and angioedema have been reported postmarketing. Discontinue WEGOVY if suspected and promptly seek medical advice (5.6).
- Diabetic Retinopathy Complications in Patients with Type 2 Diabetes: Has been reported in trials with semaglutide. Patients with a history of diabetic retinopathy should be monitored (5.7).
- Heart Rate Increase: Monitor heart rate at regular intervals (5.8).
- Suicidal Behavior and Ideation: Monitor for depression or suicidal thoughts. Discontinue WEGOVY if symptoms develop (5.9).

6 ADVERSE REACTIONS

Most common adverse reactions (incidence ≥ 5%) in adults or pediatric patients aged 12 years and older are: nausea, diarrhea, vomiting, constipation, abdominal pain, headache, fatigue, dyspepsia, dizziness, abdominal distension, eructation, hypoglycemia in patients with type 2 diabetes, flatulence, gastroenteritis, gastroesophageal reflux disease, and nasopharyngitis (6.1).

To report SUSPECTED ADVERSE REACTIONS, contact Novo Nordisk Inc., at 1-833-934-6891 or FDA at 1-800-FDA-1088 or www.fda.gov/medwatch.

7 DRUG INTERACTIONS

WEGOVY delays gastric emptying. May impact absorption of concomitantly administered oral medications. Use with caution (7.2).

8 USE IN SPECIFIC POPULATIONS

- Pregnancy: May cause fetal harm. When pregnancy is recognized, discontinue WEGOVY (8.1).
- Females and Males of Reproductive Potential: Discontinue WEGOVY at least 2 months before a planned pregnancy because of the long half-life of semaglutide (8.3).

FULL PRESCRIBING INFORMATION

WARNING: RISK OF THYROID C-CELL TUMORS

- In rodents, semaglutide causes dose-dependent and treatment-duration-dependent thyroid C-cell tumors at clinically relevant exposures. It is unknown whether WEGOVY causes thyroid C-cell tumors, including medullary thyroid carcinoma (MTC), in humans as human relevance of semaglutide-induced rodent thyroid C-cell tumors has not been determined [see Warnings and Precautions (5.1) and Nonclinical Toxicology (13.1)].
- WEGOVY is contraindicated in patients with a personal or family history of MTC or in patients with Multiple Endocrine Neoplasia syndrome type 2 (MEN 2) [see Contraindications (4)]. Counsel patients regarding the potential risk for MTC with the use of WEGOVY and inform them of symptoms of thyroid tumors (e.g. a mass in the neck, dysphagia, dyspnea, persistent hoarseness). Routine monitoring of serum calcitonin or using thyroid ultrasound is of uncertain value for early detection of MTC in patients treated with WEGOVY [see Contraindications (4) and Warnings and Precautions (5.1)].

1 INDICATIONS AND USAGE

WEGOVY is indicated in combination with a reduced calorie diet and increased physical activity:

- to reduce the risk of major adverse cardiovascular events (cardiovascular death, non-fatal myocardial infarction, or non-fatal stroke) in adults with established cardiovascular disease and either obesity or overweight.
- to reduce excess body weight and maintain weight reduction long term in:
  - Adults and pediatric patients aged 12 years and older with obesity
- Adults with overweight in the presence of at least one weight-related comorbid condition.

Limitations of Use

- WEGOVY contains semaglutide. Coadministration with other semaglutide-containing products or with any other GLP-1 receptor agonist is not recommended.

2 DOSAGE AND ADMINISTRATION

2.1 Important Monitoring and Administration Instructions

- In patients with type 2 diabetes, monitor blood glucose prior to starting WEGOVY and during WEGOVY treatment [see Warnings and Precautions (5.4)].
- Prior to initiation of WEGOVY, train patients on proper injection technique. Refer to the accompanying Instructions for Use for complete administration instructions with illustrations.
- Inspect WEGOVY visually prior to each injection. Only use if solution is clear, colorless, and contains no particles.
- Administer WEGOVY in combination with a reduced-calorie diet and increased physical activity.
- Administer WEGOVY once weekly, on the same day each week, at any time of day, with or without meals.
- Inject WEGOVY subcutaneously in the abdomen, thigh, or upper arm. The time of day and the injection site can be changed without dose adjustment.

2.2 Recommended Dosage in Adults

Dosage Initiation and Escalation

- Initiate WEGOVY with a dosage of 0.25 mg injected subcutaneously once weekly. Then follow the dose escalation schedule presented in Table 1 to minimize gastrointestinal adverse reactions [see Adverse Reactions (6.1)].
- If patients do not tolerate a dose during dosage escalation, consider delaying dosage escalation for 4 weeks.

Table 1. Recommended Dosage Regimen for Adults

Treatment | Weeks | Once weekly Subcutaneous Dosage
Initiation | 1 through 4 | 0.25 mg
Escalation | 5 through 8 | 0.5 mg
Escalation | 9 through 12 | 1 mg
Escalation | 13 through 16 | 1.7 mg
Maintenance | 17 and onward | 1.7 mg or 2.4 mg

Maintenance Dosage

- The maintenance dosage of WEGOVY in adults is either 2.4 mg (recommended) or 1.7 mg once weekly. Consider treatment response and tolerability when selecting the maintenance dosage [see Clinical Studies (14.2)].

2.3 Recommended Dosage in Pediatric Patients Aged 12 Years and Older

Dosage Initiation and Escalation

- Initiate WEGOVY according to the dosage escalation schedule in Table 2 to minimize gastrointestinal adverse reactions [see Adverse Reactions (6.1)].
- If patients do not tolerate a dose during dosage escalation, consider delaying dosage escalation for 4 weeks.
- The 0.25 mg, 0.5 mg, and 1 mg once-weekly dosages are initiation and escalation dosages and are not approved as maintenance dosages.
  Table 2. Recommended Dosage Regimen for Pediatric Patients Aged 12 Years and Older

Treatment | Weeks | Once weekly Subcutaneous Dosage
Initiation | 1 through 4 | 0.25 mga
Escalation | 5 through 8 | 0.5 mga
Escalation | 9 through 12 | 1 mga
Escalation | 13 through 16 | 1.7 mgb
Maintenance | 17 and onward | 2.4 mg

aNot approved as maintenance dosages
bSee Dosage Modifications for Adverse Reactions

Maintenance Dosage

- The maintenance dosage of WEGOVY in pediatric patients aged 12 years and older is 2.4 mg once weekly.

Dosage Modifications for Adverse Reactions

- If patients do not tolerate the 2.4 mg once weekly maintenance dosage, the maintenance dosage may be reduced to 1.7 mg once weekly.
- Discontinue WEGOVY if the patient cannot tolerate the 1.7 mg once-weekly dosage.

2.4 Recommendations Regarding Missed Dose

- If one dose is missed and the next scheduled dose is more than 2 days away (48 hours), administer WEGOVY as soon as possible. If one dose is missed and the next scheduled dose is less than 2 days away (48 hours), do not administer the dose. Resume dosing on the regularly scheduled day of the week.
- If 2 or more consecutive doses are missed, resume dosing as scheduled or, if needed, reinitiate WEGOVY and follow the dose escalation schedule, which may reduce the occurrence of gastrointestinal symptoms associated with reinitiation of treatment.

3 DOSAGE FORMS AND STRENGTHS

Injection: clear, colorless solution available in 5 pre-filled, disposable, single-dose pens:

- 0.25 mg/0.5 mL
- 0.5 mg/0.5 mL
- 1 mg/0.5 mL
- 1.7 mg/0.75 mL
- 2.4 mg/0.75 mL

4 CONTRAINDICATIONS

WEGOVY is contraindicated in the following conditions:

- A personal or family history of MTC or in patients with MEN 2 [see Warnings and Precautions (5.1)].
- A prior serious hypersensitivity reaction to semaglutide or to any of the excipients in WEGOVY. Serious hypersensitivity reactions, including anaphylaxis and angioedema, have been reported with WEGOVY [see Warnings and Precautions (5.6)].

5 WARNINGS AND PRECAUTIONS

5.1 Risk of Thyroid C-Cell Tumors

In mice and rats, semaglutide caused a dose-dependent and treatment-duration-dependent increase in the incidence of thyroid C-cell tumors (adenomas and carcinomas) after lifetime exposure at clinically relevant plasma exposures [see Nonclinical Toxicology (13.1)]. It is unknown whether WEGOVY causes thyroid C-cell tumors, including MTC, in humans, as human relevance of semaglutide-induced rodent thyroid C-cell tumors has not been determined.

Cases of MTC in patients treated with liraglutide, another GLP-1 receptor agonist, have been reported in the postmarketing period; the data in these reports are insufficient to establish or exclude a causal relationship between MTC and GLP-1 receptor agonist use in humans.

WEGOVY is contraindicated in patients with a personal or family history of MTC or in patients with MEN 2. Counsel patients regarding the potential risk for MTC with the use of WEGOVY and inform them of symptoms of thyroid tumors (e.g. a mass in the neck, dysphagia, dyspnea, persistent hoarseness).

Routine monitoring of serum calcitonin or using thyroid ultrasound is of uncertain value for early detection of MTC in patients treated with WEGOVY. Such monitoring may increase the risk of unnecessary procedures, due to the low-test specificity for serum calcitonin and a high background incidence of thyroid disease. Significantly elevated serum calcitonin value may indicate MTC and patients with MTC usually have calcitonin values greater than 50 ng/L. If serum calcitonin is measured and found to be elevated, the patient should be further evaluated. Patients with thyroid nodules noted on physical examination or neck imaging should also be further evaluated.

5.2 Acute Pancreatitis

Acute pancreatitis, including fatal and non-fatal hemorrhagic or necrotizing pancreatitis, has been observed in patients treated with GLP-1 receptor agonists, including semaglutide. Acute pancreatitis was observed in patients treated with WEGOVY in clinical trials [see Adverse Reactions (6)]. After initiation of WEGOVY, observe patients carefully for signs and symptoms of acute pancreatitis (including persistent severe abdominal pain, sometimes radiating to the back, and which may or may not be accompanied by vomiting). If acute pancreatitis is suspected, WEGOVY should promptly be discontinued, and appropriate management should be initiated. If acute pancreatitis is confirmed, WEGOVY should not be restarted.

There is limited experience from clinical trials with WEGOVY in patients with a history of pancreatitis. It is unknown if patients with a history of pancreatitis are at higher risk for development of pancreatitis on WEGOVY.

5.3 Acute Gallbladder Disease

Treatment with WEGOVY is associated with an increased occurrence of cholelithiasis and cholecystitis. The incidence of cholelithiasis and cholecystitis was higher in WEGOVY-treated pediatric patients aged 12 years and older than in WEGOVY-treated adults. In randomized clinical trials in adult patients, cholelithiasis was reported by 1.6% of WEGOVY-treated patients and 0.7% of placebo-treated patients. Cholecystitis was reported by 0.6% of WEGOVY-treated adult patients and 0.2% of placebo-treated patients. In a clinical trial in pediatric patients aged 12 years and older, cholelithiasis was reported by 3.8% of WEGOVY-treated patients and 0% placebo-treated patients. Cholecystitis was reported by 0.8% of WEGOVY-treated pediatric patients and 0% placebo-treated patients [see Adverse Reactions (6.1)].

Substantial or rapid weight loss can increase the risk of cholelithiasis; however, the incidence of acute gallbladder disease was greater in WEGOVY-treated patients than in placebo-treated patients, even after accounting for the degree of weight loss. If cholelithiasis is suspected, gallbladder studies and appropriate clinical follow-up are indicated.

5.4 Hypoglycemia

WEGOVY lowers blood glucose and can cause hypoglycemia.

In a trial of adult patients with type 2 diabetes and body mass index (BMI) greater than or equal to 27 kg/m^2, hypoglycemia (defined as a plasma glucose less than 54 mg/dL) was reported in 6.2% of WEGOVY-treated patients versus 2.5% of placebo-treated patients. One episode of severe hypoglycemia (requiring the assistance of another person) was reported in one WEGOVY-treated patient versus no placebo-treated patients.

Patients with diabetes mellitus taking WEGOVY in combination with insulin or an insulin secretagogue (e.g., sulfonylurea) may have an increased risk of hypoglycemia, including severe hypoglycemia. Hypoglycemia has been observed in patients treated with semaglutide at doses of 0.5 and 1 mg in combination with insulin. The use of WEGOVY (semaglutide 2.4 mg or 1.7 mg once weekly) in patients with type 1 diabetes mellitus or in combination with insulin has not been evaluated.

Inform patients of the risk of hypoglycemia and educate them on the signs and symptoms of hypoglycemia. In patients with diabetes, monitor blood glucose prior to starting WEGOVY and during WEGOVY treatment. When initiating WEGOVY, consider reducing the dose of concomitantly administered insulin or insulin secretagogue (such as sulfonylureas) to reduce the risk of hypoglycemia [see Drug Interactions (7)].

5.5 Acute Kidney Injury

There have been postmarketing reports of acute kidney injury and worsening of chronic renal failure, which have in some cases required hemodialysis, in patients treated with semaglutide. Patients with renal impairment may be at greater risk of acute kidney injury, but some of these events have been reported in patients without known underlying renal disease. A majority of the reported events occurred in patients who had experienced nausea, vomiting, or diarrhea, leading to volume depletion [see Adverse Reactions (6)].

Monitor renal function when initiating or escalating doses of WEGOVY in patients reporting severe adverse gastrointestinal reactions. Monitor renal function in patients with renal impairment reporting any adverse reactions that could lead to volume depletion.

5.6 Hypersensitivity Reactions

Serious hypersensitivity reactions (e.g., anaphylaxis, angioedema) have been reported with WEGOVY. If hypersensitivity reactions occur, discontinue use of WEGOVY, treat promptly per standard of care, and monitor until signs and symptoms resolve. WEGOVY is contraindicated in patients with a prior serious hypersensitivity reaction to semaglutide or to any of the excipients in WEGOVY [see Adverse Reactions (6.2)].

Anaphylaxis and angioedema have been reported with other GLP-1 receptor agonists. Use caution in a patient with a history of anaphylaxis or angioedema with another GLP-1 receptor agonist because it is unknown whether such patients will be predisposed to these reactions with WEGOVY.

5.7 Diabetic Retinopathy Complications in Patients with Type 2 Diabetes

In a trial of adult patients with type 2 diabetes and BMI greater than or equal to 27 kg/m^2, diabetic retinopathy was reported by 4.0% of WEGOVY-treated patients and 2.7% placebo-treated patients.

In a 2-year trial with semaglutide 0.5 mg and 1 mg once-weekly injection in adult patients with type 2 diabetes and high cardiovascular risk, diabetic retinopathy complications (which was a 4-component adjudicated endpoint) occurred in patients treated with semaglutide injection (3.0%) compared to placebo (1.8%). The absolute risk increase for diabetic retinopathy complications was larger among patients with a history of diabetic retinopathy at baseline (semaglutide injection 8.2%, placebo 5.2%) than among patients without a known history of diabetic retinopathy (semaglutide injection 0.7%, placebo 0.4%).

Rapid improvement in glucose control has been associated with a temporary worsening of diabetic retinopathy. The effect of long-term glycemic control with semaglutide on diabetic retinopathy complications has not been studied. Patients with a history of diabetic retinopathy should be monitored for progression of diabetic retinopathy.

5.8 Heart Rate Increase

Treatment with WEGOVY was associated with increases in resting heart rate. Mean increases in resting heart rate of 1 to 4 beats per minute (bpm) were observed in WEGOVY-treated adult patients compared to placebo in clinical trials. More adult patients treated with WEGOVY compared with placebo had maximum changes from baseline at any visit of 10 to 19 bpm (41% versus 34%, respectively) and 20 bpm or more (26% versus 16%, respectively). In a clinical trial in pediatric patients aged 12 years and older with normal baseline heart rate, more patients treated with WEGOVY compared to placebo had maximum changes in heart rate of 20 bpm or more (54% versus 39%) [see Adverse Reactions (6.1)].

Monitor heart rate at regular intervals consistent with usual clinical practice. Instruct patients to inform their healthcare providers of palpitations or feelings of a racing heartbeat while at rest during WEGOVY treatment. If patients experience a sustained increase in resting heart rate, discontinue WEGOVY.

5.9 Suicidal Behavior and Ideation

Suicidal behavior and ideation have been reported in clinical trials with other weight management products. Monitor patients treated with WEGOVY for the emergence or worsening of depression, suicidal thoughts or behavior, and/or any unusual changes in mood or behavior. Discontinue WEGOVY in patients who experience suicidal thoughts or behaviors. Avoid WEGOVY in patients with a history of suicidal attempts or active suicidal ideation.

6 ADVERSE REACTIONS

The following serious adverse reactions are described below or elsewhere in the prescribing information:

- Risk of Thyroid C-Cell Tumors [see Warnings and Precautions (5.1)]
- Acute Pancreatitis [see Warnings and Precautions (5.2)]
- Acute Gallbladder Disease [see Warnings and Precautions (5.3)]
- Hypoglycemia [see Warnings and Precautions (5.4)]
- Acute Kidney Injury [see Warnings and Precautions (5.5)]
- Hypersensitivity Reactions [see Warnings and Precautions (5.6)]
- Diabetic Retinopathy Complications in Patients with Type 2 Diabetes [see Warnings and Precautions (5.7)]
- Heart Rate Increase [see Warnings and Precautions (5.8)]
- Suicidal Behavior and Ideation [see Warnings and Precautions (5.9)]

6.1 Clinical Trials Experience

Because clinical trials are conducted under widely varying conditions, adverse reaction rates observed in the clinical trials of a drug cannot be directly compared to rates in the clinical studies of another drug and may not reflect the rates observed in practice.

Adverse Reactions in Clinical Trials in Adults with Obesity or Overweight

WEGOVY 2.4 mg Subcutaneous Weekly Dosage

WEGOVY was evaluated for safety in 3 randomized, double-blind, placebo-controlled trials that included 2,116 adult patients with obesity or overweight treated with 2.4 mg WEGOVY for up to 68 weeks and a 7 week off-drug follow-up period [see Clinical Studies (14.2)]. Baseline characteristics included a mean age of 48 years, 71% female, 72% White, 14% Asian, 9% Black or African American, and 5% reported as other or unknown; and 85% were not Hispanic or Latino ethnicity, 13% were Hispanic or Latino ethnicity, and 2% reported as unknown. The baseline characteristics were 42% with hypertension, 19% with type 2 diabetes, 43% with dyslipidemia, 28% with a BMI greater than 40 kg/m^2, and 4% with cardiovascular disease.

In these clinical trials, 6.8% of patients treated with 2.4 mg WEGOVY and 3.2% of patients treated with placebo permanently discontinued treatment as a result of adverse reactions. The most common adverse reactions leading to discontinuation were nausea (1.8% versus 0.2%), vomiting (1.2% versus 0%), and diarrhea (0.7% versus 0.1%) for WEGOVY and placebo, respectively.

Adverse reactions reported in clinical trials in adults and greater than or equal to 2% of WEGOVY-treated patients and more frequently than in placebo-treated patients are shown in Table 3.

Table 3. Adverse Reactions (≥2% and Greater Than Placebo) in WEGOVY-treated Adults with Obesity or Overweight

 | Placebo; N = 1,261; % | WEGOVY 2.4 mg; N = 2,116; %
Nausea | 16 | 44
Diarrhea | 16 | 30
Vomiting | 6 | 24
Constipation | 11 | 24
Abdominal Paina | 10 | 20
Headache | 10 | 14
Fatigueb | 5 | 11
Dyspepsia | 3 | 9
Dizziness | 4 | 8
Abdominal Distension | 5 | 7
Eructation | <1 | 7
Hypoglycemia in T2DMc | 2 | 6
Flatulence | 4 | 6
Gastroenteritis | 4 | 6
Gastroesophageal Reflux Disease | 3 | 5
Gastritisd | 1 | 4
Gastroenteritis Viral | 3 | 4
Hair Loss | 1 | 3
Dysesthesiae | 1 | 2

aIncludes abdominal pain, abdominal pain upper, abdominal pain lower, gastrointestinal pain, abdominal tenderness, abdominal discomfort and epigastric discomfort

bIncludes fatigue and asthenia

cDefined as blood glucose <54 mg/dL with or without symptoms of hypoglycemia or severe hypoglycemia (requiring the assistance of another person) in patients with type 2 diabetes not on concomitant insulin (Study 3, WEGOVY N=403, Placebo N=402). See text below for further information regarding hypoglycemia in patients with and without type 2 diabetes. T2DM = type 2 diabetes mellitus

dIncludes chronic gastritis, gastritis, gastritis erosive, and reflux gastritis
eIncludes paresthesia, hyperesthesia, burning sensation, allodynia, dysesthesia, skin burning sensation, pain of skin, and sensitive skin

In a cardiovascular outcomes trial, 8,803 patients were exposed to WEGOVY for a median of 37.3 months and 8,801 patients were exposed to placebo for a median of 38.6 months [see Clinical Studies (14.1)]. Safety data collection was limited to serious adverse events (including death), adverse events leading to discontinuation, and adverse events of special interest. Sixteen percent (16%) of WEGOVY-treated patients and 8% of placebo-treated patients, respectively, discontinued study drug due to an adverse event. Additional information from this trial is included in subsequent sections below when relevant.

Adverse Reactions in a Clinical Trial of Pediatric Patients Aged 12 Years and Older with Obesity

WEGOVY was evaluated in a 68-week, double-blind, randomized, parallel group, placebo-controlled, multi-center trial in 201 pediatric patients aged 12 years and older with obesity [see Clinical Studies (14.3)]. Baseline characteristics included a mean age of 15.4 years; 38% of patients were male; 79% were White, 8% were Black or African American, 2% were Asian, and 11% were of other or unknown race; and 11% were of Hispanic or Latino ethnicity. The mean baseline body weight was 107.5 kg, and mean BMI was 37 kg/m^2.

Table 4 shows adverse reactions reported in greater than or equal to 3% of WEGOVY-treated pediatric patients and more frequently than in the placebo group from a study in pediatric patients aged 12 years and older.

Table 4. Adverse Reactions (≥3% and Greater than Placebo) in WEGOVY-Treated Pediatric Patients Aged 12 Years and Older with Obesity

 | Placebo N = 67 % | WEGOVY 2.4 mg N = 133 %
Nausea | 18 | 42
Vomiting | 10 | 36
Diarrhea | 19 | 22
Headache | 16 | 17
Abdominal Pain | 6 | 15
Nasopharyngitis | 10 | 12
Dizziness | 3 | 8
Gastroenteritis | 3 | 7
Constipation | 2 | 6
Gastroesophageal Reflux Disease | 2 | 4
Sinusitis | 2 | 4
Urinary tract infection | 2 | 4
Ligament sprain | 2 | 4
Anxiety | 2 | 4
Hair Loss | 0 | 4
Cholelithiasis | 0 | 4
Eructation | 0 | 4
Influenza | 0 | 3
Rash | 0 | 3
Urticaria | 0 | 3

Other Adverse Reactions in Adults and/or Pediatric Patients

Acute Pancreatitis

In WEGOVY clinical trials in adults, acute pancreatitis was confirmed by adjudication in 4 WEGOVY-treated patients (0.2 cases per 100 patient years) versus 1 in placebo-treated patients (less than 0.1 cases per 100 patient years). One additional case of acute pancreatitis was confirmed in a patient treated with WEGOVY in another clinical trial.

Acute Gallbladder Disease

In WEGOVY clinical trials in adults, cholelithiasis was reported by 1.6% of WEGOVY-treated patients and 0.7% of placebo-treated patients. Cholecystitis was reported by 0.6% of WEGOVY-treated adult patients and 0.2% of placebo-treated patients. In a clinical trial in pediatric patients aged 12 years and older [see Clinical Studies (14.3)], cholelithiasis was reported by 3.8% of WEGOVY-treated patients and 0% placebo-treated patients. Cholecystitis was reported by 0.8% of WEGOVY-treated pediatric patients and 0% placebo-treated patients.

Hypoglycemia

Patients with Type 2 Diabetes

In a trial of adult patients with type 2 diabetes and BMI greater than or equal to 27 kg/m^2, clinically significant hypoglycemia (defined as a plasma glucose less than 54 mg/dL) was reported in 6.2% of WEGOVY-treated patients versus 2.5% of placebo-treated patients. A higher rate of clinically significant hypoglycemic episodes was reported with WEGOVY (semaglutide 2.4 mg) versus semaglutide 1 mg (10.7 vs. 7.2 episodes per 100 patient years of exposure, respectively); the rate in the placebo-treated group was 3.2 episodes per 100 patient years of exposure. In addition, one episode of severe hypoglycemia requiring intravenous glucose was reported in a WEGOVY-treated patient versus none in placebo-treated patients. The risk of hypoglycemia was increased when WEGOVY was used with a sulfonylurea.

Patients without Type 2 Diabetes

Episodes of hypoglycemia have been reported with GLP-1 receptor agonists in adult patients without type 2 diabetes mellitus. In WEGOVY clinical trials in adult patients without type 2 diabetes mellitus, there was no systematic capturing or reporting of hypoglycemia.

In a cardiovascular outcomes trial in adult patients without type 2 diabetes, 3 episodes of serious hypoglycemia were reported in WEGOVY-treated patients versus 1 episode in placebo. Patients with a history of bariatric surgery (a risk factor for hypoglycemia) had more events of serious hypoglycemia while taking WEGOVY (2.3%, 2/87) than placebo (0%, 0/97).

Acute Kidney Injury

Acute kidney injury occurred in clinical trials in 7 adult patients (0.4 cases per 100 patient years) receiving WEGOVY versus 4 patients (0.2 cases per 100 patient years of exposure) receiving placebo. Some of these adverse reactions occurred in association with gastrointestinal adverse reactions or dehydration. In addition, 2 patients treated with WEGOVY had acute kidney injury with dehydration in other clinical trials. The risk of renal adverse reactions with WEGOVY was increased in adult patients with a history of renal impairment (trials included 65 patients with a history of moderate or severe renal impairment at baseline), and occurred more frequently during dose titration.

Retinal Disorders in Patients with Type 2 Diabetes

In a trial of adult patients with type 2 diabetes and BMI greater than or equal to 27 kg/m^2, retinal disorders were reported by 6.9% of patients treated with WEGOVY (semaglutide 2.4 mg), 6.2% of patients treated with semaglutide 1 mg, and 4.2% of patients treated with placebo. The majority of events were reported as diabetic retinopathy (4.0%, 2.7%, and 2.7%, respectively) and non-proliferative retinopathy (0.7%, 0%, and 0%, respectively).

Increase in Heart Rate

Mean increases in resting heart rate of 1 to 4 beats per minute (bpm) were observed with routine clinical monitoring in WEGOVY-treated adult patients compared to placebo in clinical trials. In trials in which adult patients were randomized prior to dose-escalation, more patients treated with WEGOVY, compared with placebo, had maximum changes from baseline at any visit of 10 to 19 bpm (41% versus 34%, respectively) and 20 bpm or more (26% versus 16%, respectively). In a clinical trial in pediatric patients aged 12 years and older with normal baseline heart rate, more patients treated with WEGOVY compared to placebo had maximum changes in heart rate of 20 bpm or more (54% versus 39%).

Hypotension and Syncope

Adverse reactions related to hypotension (hypotension, orthostatic hypotension, and decreased blood pressure) were reported in 1.3% of WEGOVY-treated adult patients versus 0.4% of placebo-treated patients and syncope was reported in 0.8% of WEGOVY-treated patients versus 0.2% of placebo-treated patients. Some reactions were related to gastrointestinal adverse reactions and volume loss associated with WEGOVY. Hypotension and orthostatic hypotension were more frequently seen in patients on concomitant antihypertensive therapy. In a clinical trial in pediatric patients aged 12 years and older, hypotension was reported in 2.3% of WEGOVY-treated patients versus 0% in placebo-treated patients.

Appendicitis

Appendicitis (including perforated appendicitis) occurred in 10 (0.5%) WEGOVY-treated adult patients and 2 (0.2%) patients receiving placebo.

Gastrointestinal Adverse Reactions

In clinical trials in adults, 73% of WEGOVY-treated patients and 47% of patients receiving placebo reported gastrointestinal adverse reactions, including severe reactions that were reported more frequently among patients receiving WEGOVY (4.1%) than placebo (0.9%). The most frequently reported reactions were nausea (44% vs. 16%), vomiting (25% vs. 6%), and diarrhea (30% vs. 16%). Other reactions that occurred at a higher incidence among WEGOVY-treated adult patients included dyspepsia, abdominal pain, abdominal distension, eructation, flatulence, gastroesophageal reflux disease, gastritis, hemorrhoids, and hiccups. These reactions increased during dose escalation.

In the pediatric clinical trial, 62% of WEGOVY-treated patients and 42% of placebo-treated patients reported gastrointestinal disorders. The most frequently reported reactions were nausea (42% vs. 18%), vomiting (36% vs. 10%), and diarrhea (22% vs. 19%). Other gastrointestinal-related reactions that occurred at a higher incidence than placebo among WEGOVY-treated pediatric patients included abdominal pain, constipation, eructation, gastroesophageal reflux disease, dyspepsia, and flatulence.

Permanent discontinuation of treatment as a result of a gastrointestinal adverse reaction occurred in 4.3% of WEGOVY-treated adult patients versus 0.7% of placebo-treated patients. In a pediatric clinical trial, 2.3% of patients treated with WEGOVY versus 1.5% of patients who received placebo discontinued treatment as a result of gastrointestinal adverse reactions.

Injection Site Reactions

In clinical trials in adults, 1.4% of WEGOVY-treated patients and 1.0% of patients receiving placebo experienced injection site reactions (including injection site pruritus, erythema, inflammation, induration, and irritation).

Hypersensitivity Reactions

Serious hypersensitivity reactions (e.g., anaphylaxis, angioedema) have been reported with WEGOVY.

In a pediatric clinical trial, rash was reported in 3% of WEGOVY-treated patients and 0% of placebo-treated patients, and urticaria was reported in 3% of WEGOVY-treated patients and 0% of placebo-treated patients.

In adult clinical trials, allergic reactions occurred in 16% (8/50) of WEGOVY-treated patients with anti-semaglutide antibodies and in 7% (114/1659) of WEGOVY-treated patients who did not develop anti-semaglutide antibodies [see Clinical Pharmacology (12.6)].

Fractures

In the cardiovascular outcomes trial in adults, more fractures of the hip and pelvis were reported on WEGOVY than on placebo in female patients: 1.0% (24/2448) vs. 0.2% (5/2424), and in patients ages 75 years and older: 2.4% (17/703) vs. 0.6% (4/663), respectively.

Urolithiasis

In a cardiovascular outcomes trial, 1.2% of WEGOVY-treated patients and 0.8% of patients receiving placebo reported urolithiasis, including serious reactions that were reported more frequently among patients receiving WEGOVY (0.6%) than placebo (0.4%).

Dysgeusia

In clinical trials in adults, 1.7% of WEGOVY-treated patients and 0.5% of placebo-treated patients reported dysgeusia.

Laboratory Abnormalities

Amylase and Lipase

Adult and pediatric patients treated with WEGOVY had a mean increase from baseline in amylase of 15-16% and lipase of 39%. These changes were not observed in the placebo group. The clinical significance of elevations in lipase or amylase with WEGOVY is unknown in the absence of other signs and symptoms of pancreatitis.

Liver Enzymes

In a pediatric clinical trial, increases in alanine aminotransferase (ALT) greater than or equal to 5 times the upper limit of normal were observed in 4 (3%) WEGOVY-treated patients compared with 0% of placebo-treated patients. In some patients, increases in ALT and AST were associated with other confounding factors (such as gallstones). In the cardiovascular outcomes trial in adults, increases in total bilirubin greater than or equal to 3 times the upper limit of normal were observed in 0.3% (30/8585) of WEGOVY-treated patients versus 0.2% (14/8579) of placebo-treated patients.

6.2 Postmarketing Experience

The following adverse reactions have been reported during post-approval use of semaglutide, the active ingredient of WEGOVY. Because these reactions are reported voluntarily from a population of uncertain size, it is not always possible to reliably estimate their frequency or establish a causal relationship to drug exposure.

Gastrointestinal Disorders: acute pancreatitis and necrotizing pancreatitis, sometimes resulting in death; ileus

Hypersensitivity: anaphylaxis, angioedema, rash, urticaria

Renal and Urinary Disorders: acute kidney injury

7 DRUG INTERACTIONS

7.1 Concomitant Use with Insulin or an Insulin Secretagogue (e.g., Sulfonylurea)

WEGOVY lowers blood glucose and can cause hypoglycemia. The risk of hypoglycemia is increased when WEGOVY is used in combination with insulin or insulin secretagogues (e.g., sulfonylureas). The addition of WEGOVY in patients treated with insulin has not been evaluated.

When initiating WEGOVY, consider reducing the dose of concomitantly administered insulin secretagogue (such as sulfonylureas) or insulin to reduce the risk of hypoglycemia [see Warnings and Precautions (5.4) and Adverse Reactions (6.1)].

7.2 Oral Medications

WEGOVY causes a delay of gastric emptying and thereby has the potential to impact the absorption of concomitantly administered oral medications. In clinical pharmacology trials with semaglutide 1 mg, semaglutide did not affect the absorption of orally administered medications [see Clinical Pharmacology (12.3)]. Nonetheless, monitor the effects of oral medications concomitantly administered with WEGOVY.

8 USE IN SPECIFIC POPULATIONS

8.1 Pregnancy

Pregnancy Exposure Registry

There will be a pregnancy exposure registry that monitors pregnancy outcomes in women exposed to semaglutide during pregnancy. Pregnant women exposed to WEGOVY and healthcare providers are encouraged to contact Novo Nordisk at 1-877-390-2760 or www.wegovypregnancyregistry.com.

Risk Summary

Based on animal reproduction studies, there may be potential risks to the fetus from exposure to semaglutide during pregnancy. Additionally, weight loss offers no benefit to a pregnant patient and may cause fetal harm. When a pregnancy is recognized, advise the pregnant patient of the risk to a fetus, and discontinue WEGOVY (see Clinical Considerations). Available pharmacovigilance data and data from clinical trials with WEGOVY use in pregnant patients are insufficient to establish a drug-associated risk of major birth defects, miscarriage or adverse maternal or fetal outcomes.

In pregnant rats administered semaglutide during organogenesis, embryofetal mortality, structural abnormalities and alterations to growth occurred at maternal exposures below the maximum recommended human dose (MRHD) based on AUC. In rabbits and cynomolgus monkeys administered semaglutide during organogenesis, early pregnancy losses and structural abnormalities were observed at below the MRHD (rabbit) and greater than or equal to 2-fold the MRHD (monkey). These findings coincided with a marked maternal body weight loss in both animal species (see Data).

The estimated background risk of major birth defects and miscarriage for the indicated population are unknown. In the U.S. general population, the estimated background risk of major birth defects and miscarriage in clinically recognized pregnancies is 2-4% and 15-20%, respectively.

Clinical Considerations

Disease-associated maternal and/or embryo/fetal risk

Appropriate weight gain based on pre-pregnancy weight is currently recommended for all pregnant patients, including those who already have overweight or obesity, because of the obligatory weight gain that occurs in maternal tissues during pregnancy.

Data

Animal Data

In a combined fertility and embryofetal development study in rats, subcutaneous doses of 0.01, 0.03 and 0.09 mg/kg/day (0.04-, 0.1-, and 0.4-fold the MRHD) were administered to males for 4 weeks prior to and throughout mating and to females for 2 weeks prior to mating, and throughout organogenesis to Gestation Day 17. In parental animals, pharmacologically mediated reductions in body weight gain and food consumption were observed at all dose levels. In the offspring, reduced growth and fetuses with visceral (heart blood vessels) and skeletal (cranial bones, vertebra, ribs) abnormalities were observed at the human exposure.

In an embryofetal development study in pregnant rabbits, subcutaneous doses of 0.0010, 0.0025 or 0.0075 mg/kg/day (0.01-, 0.1-, and 0.9-fold the MRHD) were administered throughout organogenesis from Gestation Day 6 to 19. Pharmacologically mediated reductions in maternal body weight gain and food consumption were observed at all dose levels. Early pregnancy losses and increased incidences of minor visceral (kidney, liver) and skeletal (sternebra) fetal abnormalities were observed at greater than or equal to 0.0025 mg/kg/day, at clinically relevant exposures.

In an embryofetal development study in pregnant cynomolgus monkeys, subcutaneous doses of 0.015, 0.075, and 0.15 mg/kg twice weekly (0.4-, 2-, and 6-fold the MRHD) were administered throughout organogenesis, from Gestation Day 16 to 50. Pharmacologically mediated, marked initial maternal body weight loss and reductions in body weight gain and food consumption coincided with the occurrence of sporadic abnormalities (vertebra, sternebra, ribs) at greater than or equal to 0.075 mg/kg twice weekly (greater than or equal to 2 times human exposure).

In a pre- and postnatal development study in pregnant cynomolgus monkeys, subcutaneous doses of 0.015, 0.075, and 0.15 mg/kg twice weekly (0.2-, 1-, and 3-fold the MRHD) were administered from Gestation Day 16 to 140. Pharmacologically mediated marked initial maternal body weight loss and reductions in body weight gain and food consumption coincided with an increase in early pregnancy losses and led to delivery of slightly smaller offspring at greater than or equal to 0.075 mg/kg twice weekly (greater than or equal to 1-time human exposure).

8.2 Lactation

Risk Summary

There are no data on the presence of semaglutide or its metabolites in human milk, the effects on the breastfed infant, or the effects on milk production. Semaglutide was present in the milk of lactating rats. When a drug is present in animal milk, it is likely that the drug will be present in human milk (see Data). The developmental and health benefits of breastfeeding should be considered along with the mother’s clinical need for WEGOVY and any potential adverse effects on the breastfed infant from WEGOVY or from the underlying maternal condition.

Data

In lactating rats, semaglutide was detected in milk at levels 3-12-fold lower than in maternal plasma.

8.3 Females and Males of Reproductive Potential

Because of the potential for fetal harm, discontinue WEGOVY in patients at least 2 months before they plan to become pregnant to account for the long half-life of semaglutide [see Use in Specific Populations (8.1)].

8.4 Pediatric Use

The safety and effectiveness of WEGOVY as an adjunct to a reduced calorie diet and increased physical activity for weight reduction and long-term maintenance have been established in pediatric patients aged 12 years and older with obesity. Use of WEGOVY for this indication is supported by a 68-week, double-blind, placebo-controlled clinical trial in 201 pediatric patients aged 12 years and older with a BMI corresponding to ≥95th percentile for age and sex and from studies in adult patients with obesity [see Clinical Studies (14.3)].

Adverse reactions with WEGOVY treatment in pediatric patients aged 12 years and older were generally similar to those reported in adults. Pediatric patients aged 12 years and older treated with WEGOVY had greater incidences of cholelithiasis, cholecystitis, hypotension, rash, and urticaria compared to adults treated with WEGOVY [see Adverse Reactions (6.1)].

There are insufficient data in pediatric patients with type 2 diabetes treated with WEGOVY for obesity to determine if there is an increased risk of hypoglycemia with WEGOVY treatment similar to that reported in adults. Inform patients of the risk of hypoglycemia and educate them on the signs and symptoms of hypoglycemia. In pediatric patients aged 12 years and older with type 2 diabetes, monitor blood glucose prior to starting WEGOVY and during WEGOVY treatment. When initiating WEGOVY in pediatric patients aged 12 years and older with type 2 diabetes, consider reducing the dose of concomitantly administered insulin secretagogue (such as sulfonylureas) or insulin to reduce the risk of hypoglycemia [see Warnings and Precautions (5.4)].

The safety and effectiveness of WEGOVY have not been established in pediatric patients less than 12 years of age.

8.5 Geriatric Use

In the WEGOVY clinical trials for weight reduction and long-term maintenance, 233 (9%) WEGOVY-treated patients were aged 65 to 75 years and 23 (1%) WEGOVY-treated patients were aged 75 years and older [see Clinical Studies (14.2)]. In a cardiovascular outcomes trial, 2656 (30%) WEGOVY-treated patients were aged 65 to 75 years and 703 (8%) WEGOVY-treated patients were aged 75 years and older [see Clinical Studies (14.1)]. No overall difference in effectiveness was observed between patients aged 65 years and older and younger adult patients. In the cardiovascular outcomes trial, patients aged 75 years and older reported more fractures of the hip and pelvis on WEGOVY than on placebo. Patients aged 75 years and older (WEGOVY-treated and placebo-treated) reported more serious adverse reactions overall compared to younger adult patients [see Adverse Reactions (6.1)].

8.6 Renal Impairment

No dose adjustment of WEGOVY is recommended for patients with renal impairment. In a study in patients with renal impairment, including end-stage renal disease, no clinically relevant change in semaglutide pharmacokinetics was observed [see Clinical Pharmacology (12.3)].

8.7 Hepatic Impairment

No dose adjustment of WEGOVY is recommended for patients with hepatic impairment. In a study in patients with different degrees of hepatic impairment, no clinically relevant change in semaglutide pharmacokinetics was observed [see Clinical Pharmacology (12.3)].

10 OVERDOSAGE

Overdoses have been reported with other GLP-1 receptor agonists. Effects have included severe nausea, severe vomiting, and severe hypoglycemia. In the event of overdose, appropriate supportive treatment should be initiated according to the patient’s clinical signs and symptoms. In the event of an overdose of WEGOVY, consider contacting the Poison Help line (1-800-222-1222) or a medical toxicologist for additional overdosage management recommendations. A prolonged period of observation and treatment for these symptoms may be necessary, taking into account the long half-life of WEGOVY of approximately 1 week.

11 DESCRIPTION

WEGOVY (semaglutide) injection, for subcutaneous use, contains semaglutide, a human GLP-1 receptor agonist (or GLP-1 analog). The peptide backbone is produced by yeast fermentation. The main protraction mechanism of semaglutide is albumin binding, facilitated by modification of position 26 lysine with a hydrophilic spacer and a C18 fatty di-acid. Furthermore, semaglutide is modified in position 8 to provide stabilization against degradation by the enzyme dipeptidyl-peptidase 4 (DPP-4). A minor modification was made in position 34 to ensure the attachment of only one fatty di-acid. The molecular formula is C187H291N45O59 and the molecular weight is 4113.58 g/mol.

Figure 1. Structural Formula of semaglutide

WEGOVY is a sterile, aqueous, clear, colorless solution. Each 0.5 mL single-dose pen contains a solution of WEGOVY containing 0.25 mg, 0.5 mg or 1 mg of semaglutide; and each 0.75 mL single-dose pen contains a solution of WEGOVY containing 1.7 or 2.4 mg of semaglutide. Each 1 mL of WEGOVY contains the following inactive ingredients: disodium phosphate dihydrate, 1.42 mg; sodium chloride, 8.25 mg; and water for injection. WEGOVY has a pH of approximately 7.4. Hydrochloric acid or sodium hydroxide may be added to adjust pH.

12 CLINICAL PHARMACOLOGY

12.1 Mechanism of Action

Semaglutide is a GLP-1 analogue with 94% sequence homology to human GLP-1. Semaglutide acts as a GLP-1 receptor agonist that selectively binds to and activates the GLP-1 receptor, the target for native GLP-1.

GLP-1 is a physiological regulator of appetite and caloric intake, and the GLP-1 receptor is present in several areas of the brain involved in appetite regulation. Animal studies show that semaglutide distributed to and activated neurons in brain regions involved in regulation of food intake.

The exact mechanism of cardiovascular risk reduction has not been established.

12.2 Pharmacodynamics

Semaglutide lowers body weight with greater fat mass loss than lean mass loss. Semaglutide decreases calorie intake. The effects are likely mediated by affecting appetite.

Semaglutide stimulates insulin secretion and reduces glucagon secretion in a glucose-dependent manner. These effects can lead to a reduction of blood glucose.

Gastric Emptying

Semaglutide delays gastric emptying.

Cardiac Electrophysiology (QTc)

The effect of semaglutide on cardiac repolarization was tested in a thorough QTc trial. Semaglutide did not prolong QTc intervals at doses up to 1.5 mg at steady state.

12.3 Pharmacokinetics

Absorption

Absolute bioavailability of semaglutide is 89%. Maximum concentration of semaglutide is reached 1 to 3 days post dose.

Similar exposure was achieved with subcutaneous administration of semaglutide in the abdomen, thigh, or upper arm.

The average semaglutide steady state concentration following subcutaneous administration of WEGOVY was approximately 75 nmol/L in patients with either obesity (BMI greater than or equal to 30 kg/m^2) or overweight (BMI greater than or equal to 27 kg/m^2). The steady state exposure of WEGOVY increased proportionally with doses up to 2.4 mg once weekly.

Distribution

The mean volume of distribution of semaglutide following subcutaneous administration in patients with obesity or overweight is approximately 12.5 L. Semaglutide is extensively bound to plasma albumin (greater than 99%) which results in decreased renal clearance and protection from degradation.

Elimination

The apparent clearance of semaglutide in patients with obesity or overweight is approximately 0.05 L/h. With an elimination half-life of approximately 1 week, semaglutide will be present in the circulation for about 5 to 7 weeks after the last dose of 2.4 mg.

Metabolism

The primary route of elimination for semaglutide is metabolism following proteolytic cleavage of the peptide backbone and sequential beta-oxidation of the fatty acid sidechain.

Excretion

The primary excretion routes of semaglutide-related material are via the urine and feces. Approximately 3% of the dose is excreted in the urine as intact semaglutide.

Specific Populations

The effects of intrinsic factors on the pharmacokinetics of semaglutide are shown in Figure 2.

Figure 2. Impact of intrinsic factors on semaglutide exposure

Data are steady-state dose-normalized average semaglutide exposures relative to a reference subject profile (non-Hispanic or Latino ethnicity, white female aged 18 to less than 65 years, with a body weight of 110 kg and normal renal function, who injected in the abdomen). Body weight categories (74 and 143 kg) represent the 5% and 95% percentiles in the dataset.

Patients with Renal Impairment

Renal impairment did not impact the exposure of semaglutide in a clinically relevant manner. The pharmacokinetics of semaglutide were evaluated following a single dose of 0.5 mg semaglutide in a study of patients with different degrees of renal impairment (mild, moderate, severe, or ESRD) compared with subjects with normal renal function. The pharmacokinetics were also assessed in subjects with overweight (BMI 27-29.9 kg/m^2) or obesity (BMI greater than or equal to 30 kg/m^2) and mild to moderate renal impairment, based on data from clinical trials.

Patients with Hepatic Impairment

Hepatic impairment did not impact the exposure of semaglutide. The pharmacokinetics of semaglutide were evaluated following a single dose of 0.5 mg semaglutide in a study of patients with different degrees of hepatic impairment (mild, moderate, severe) compared with subjects with normal hepatic function.

Drug Interactions Studies

In vitro studies have shown very low potential for semaglutide to inhibit or induce CYP enzymes, or to inhibit drug transporters.

The delay of gastric emptying with semaglutide may influence the absorption of concomitantly administered oral medications [see Drug Interactions (7.2)]. The potential effect of semaglutide on the absorption of co-administered oral medications was studied in trials at semaglutide 1 mg steady-state exposure. No clinically relevant drug-drug interactions with semaglutide (Figure 3) were observed based on the evaluated medications. In a separate study, no apparent effect on the rate of gastric emptying was observed with semaglutide 2.4 mg.

Figure 3. Impact of semaglutide 1 mg on the pharmacokinetics of co-administered medications

Relative exposure in terms of AUC and Cmax for each medication when given with semaglutide compared to without semaglutide. Metformin and oral contraceptive drug (ethinylestradiol/levonorgestrel) were assessed at steady state. Warfarin (S-warfarin/R-warfarin), digoxin and atorvastatin were assessed after a single dose.

Abbreviations: AUC: area under the curve, Cmax: maximum concentration, CI: confidence interval.

12.6 Immunogenicity

The observed incidence of anti-drug antibodies is highly dependent on the sensitivity and specificity of the assay. Differences in assay methods preclude meaningful comparisons of the incidence of anti-drug antibodies in the studies described below with the incidence of anti-drug antibodies in other studies, including those of semaglutide or of other semaglutide products.

During the 68-week treatment periods in Studies 2 and 3 [see Clinical Studies (14.2)], 50/1709 (3%) of WEGOVY-treated patients developed anti-semaglutide antibodies. Of these 50 WEGOVY-treated patients, 28 patients (2% of the total WEGOVY-treated study population) developed antibodies that cross-reacted with native GLP-1. No identified clinically significant effect of anti-semaglutide antibodies on pharmacokinetics for WEGOVY was observed. There is insufficient evidence to characterize the effects of anti-semaglutide antibodies on pharmacodynamics or effectiveness of semaglutide.

13 NONCLINICAL TOXICOLOGY

13.1 Carcinogenesis, Mutagenesis, Impairment of Fertility

In a 2-year carcinogenicity study in CD-1 mice, subcutaneous doses of 0.3, 1 and 3 mg/kg/day (2-, 8-, and 22-fold the maximum recommended human dose [MRHD] of 2.4 mg/week, based on AUC) were administered to the males, and 0.1, 0.3 and 1 mg/kg/day (0.6-, 2-, and 5-fold MRHD) were administered to the females. A statistically significant increase in thyroid C-cell adenomas and a numerical increase in C-cell carcinomas were observed in males and females at all dose levels (greater than or equal to 0.6 times human exposure).

In a 2-year carcinogenicity study in Sprague Dawley rats, subcutaneous doses of 0.0025, 0.01, 0.025 and 0.1 mg/kg/day were administered (below quantification, 0.2-, 0.4-, and 2-fold the exposure at the MRHD). A statistically significant increase in thyroid C-cell adenomas was observed in males and females at all dose levels, and a statistically significant increase in thyroid C-cell carcinomas was observed in males at greater than or equal to 0.01 mg/kg/day, at clinically relevant exposures.

Human relevance of thyroid C-cell tumors in rats is unknown and could not be determined by clinical studies or nonclinical studies [see Boxed Warning and Warnings and Precautions (5.1)]. Semaglutide was not mutagenic or clastogenic in a standard battery of genotoxicity tests (bacterial mutagenicity [Ames] human lymphocyte chromosome aberration, rat bone marrow micronucleus).

In a combined fertility and embryo-fetal development study in rats, subcutaneous doses of 0.01, 0.03 and 0.09 mg/kg/day (0.04-, 0.1-, and 0.4-fold the MRHD) were administered to male and female rats. Males were dosed for 4 weeks prior to mating, and females were dosed for 2 weeks prior to mating and throughout organogenesis until Gestation Day 17. No effects were observed on male fertility. In females, an increase in estrus cycle length was observed at all dose levels, together with a small reduction in numbers of corpora lutea at greater than or equal to 0.03 mg/kg/day. These effects were likely an adaptive response secondary to the pharmacological effect of semaglutide on food consumption and body weight.

14 CLINICAL STUDIES

14.1 Cardiovascular Outcomes Trial in Adult Patients with Cardiovascular Disease and Either Obesity or Overweight

Overview of Clinical Trial
Study 1 (NCT03574597) was a multi-national, multi-center, placebo-controlled, double-blind trial to determine the effect of WEGOVY relative to placebo on major adverse cardiovascular events (MACE) when added to current standard of care, which included management of CV risk factors and individualized healthy lifestyle counseling (including diet and physical activity). The primary endpoint, MACE, was the time to first occurrence of a three-part composite outcome which included cardiovascular death, non-fatal myocardial infarction, and non-fatal stroke.

All patients were 45 years or older, with an initial BMI of 27 kg/m^2 or greater and established cardiovascular disease (prior myocardial infarction, prior stroke, or peripheral arterial disease). Patients with a history of type 1 or type 2 diabetes were excluded. Concomitant CV therapies could be adjusted, at the discretion of the investigator, to ensure participants were treated according to the current standard of care for patients with established cardiovascular disease.

In this trial, 17,604 patients were randomized to WEGOVY or placebo. At baseline, the mean age was 62 years (range 45-93), 72% were male, 84% were White, 4% were Black or African American, and 8% were Asian, and 10% were Hispanic or Latino. Mean baseline body weight was 97 kg and mean BMI was 33 kg/m^2. At baseline, prior myocardial infarction was reported in 76% of randomized individuals, prior stroke in 23%, and peripheral arterial disease in 9%. Heart failure was reported in 24% of patients. At baseline, cardiovascular disease and risk factors were managed with lipid-lowering therapy (90%), platelet aggregation inhibitors (86%), angiotensin converting enzyme inhibitors or angiotensin II receptor blockers (74%), and beta blockers (70%). A total of 10% had moderate renal impairment (eGFR 30 to <60 mL/min/1.73m^2) and 0.4% had severe renal impairment eGFR <30 mL/min/1.73m^2.

Results

In total, 96.9% of patients completed the trial, and vital status was available for 99.4% of patients. The median follow-up duration was 41.8 months. A total of 31% of WEGOVY-treated patients and 27% of placebo-treated patients permanently discontinued study drug.

For the primary analysis, a Cox proportional hazards model was used to test for superiority. Type 1 error was controlled across multiple tests.

WEGOVY significantly reduced the risk for first occurrence of MACE. The estimated hazard ratio (95% CI) was 0.80 (0.72, 0.90) (see Figure 4 and Table 5).

Figure 4. Cumulative Incidence Function: Time to First Occurrence of MACE in Study 1

Data from the in-trial period. Cumulative incidence estimates are based on time from randomization to first EAC-confirmed cardiovascular death, non-fatal myocardial infarction, or non-fatal stroke with non-CV death modeled as competing risk using the Aalen-Johansen estimator. Patients without events of interest were censored at the end of their in-trial observation period. Time from randomization to first cardiovascular death, non-fatal myocardial infarction, or non-fatal stroke was analyzed using a Cox proportional hazards model with treatment as categorical fixed factor. The hazard ratio and confidence interval are adjusted for the group sequential design using the likelihood ratio ordering.

HR: Hazard ratio; CI: confidence interval; CV: cardiovascular

The treatment effect for the primary composite endpoint, its components, and other relevant endpoints in Study 1 are shown in Table 5.

Table 5. Treatment Effect for MACE and Other Events in Study 1

 | Patients with events; n (%)
 | Placebo; N = 8,801 | WEGOVY; N = 8,803 | Hazard Ratio; (95% CI)
Primary composite endpoint
Composite of cardiovascular death, non-fatal myocardial infarction, or non-fatal stroke^1 | 701 (8.0%) | 569 (6.5%) | 0.80 (0.72; 0.90)*^2
Key secondary endpoints
Cardiovascular death^3 | 262 (3.0%) | 223 (2.5%) | 0.85 (0.71; 1.01)
All-cause death^4 | 458 (5.2%) | 375 (4.3%) | 0.81 (0.71; 0.93)
Other secondary endpoints
Fatal or non-fatal myocardial infarction^5 | 334 (3.8%) | 243 (2.8%) | 0.72 (0.61; 0.85)
Fatal or non-fatal stroke^5 | 178 (2.0%) | 160 (1.8%) | 0.89 (0.72; 1.11)

*p-value < 0.001, one-sided p-value

^1Primary endpoint

^2Adjusted for group sequential design using the likelihood ratio ordering.

^3Cardiovascular death was the first confirmatory secondary endpoint in the testing hierarchy and superiority was not confirmed.

^4Confirmatory secondary endpoint. Not statistically significant based on the prespecified testing hierarchy.

^5Not included in the prespecified testing hierarchy for controlling type-I error.

NOTE: Time to first event was analyzed in a Cox proportional hazards model with treatment as factor. For patients with multiple events, only the first event contributed to the composite endpoint.

Table 6. Mean Changes in Anthropometry and Cardiometabolic Parameters at Week 104 in Study 1^1,2

 |  | PLACEBO |  | WEGOVY
 |  | Baseline | Change from Baseline; (LSMean) | Baseline | Change from Baseline; (LSMean) | Difference from Placebo; (LSMean)
Body Weight (kg) |  | 96.8 | -0.9^3 | 96.5 | -9.4^3 | -8.5^3
Waist Circumference (cm) |  | 111.4 | -1.0 | 111.3 | -7.6 | -6.5
Systolic Blood Pressure (mmHg) |  | 131 | -0.5 | 131 | -3.8 | -3.3
Diastolic Blood Pressure (mmHg) |  | 79 | -0.5 | 79 | -1.0 | -0.5
Heart Rate |  | 69 | 0.7 | 69 | 3.8 | 3.1
HbA1c (%) |  | 5.8 | 0.0 | 5.8 | -0.3 | -0.3
 | Baseline |  | % Change from Baseline; (LSMean) | Baseline | % Change from Baseline; (LSMean) | Relative difference from placebo (%); (LSMean)
Total Cholesterol (mg/dL)^4 | 156.0 |  | -1.9 | 155.5 | -4.6 | -2.8
LDL Cholesterol (mg/dL)^4 | 78.5 |  | -3.1 | 78.5 | -5.3 | -2.2
HDL Cholesterol (mg/dL)^4 | 44.2 |  | 0.6 | 44.1 | 4.9 | 4.2
Triglycerides (mg/dL)^4 | 139.5 |  | -3.2 | 138.6 | -18.3 | -15.6

^1Parameters listed in the table were not included in the pre-specified hierarchical testing.

^2Responses were analysed using an ANCOVA with treatment as fixed factor and baseline value as covariate. Before analysis, missing data were multiple imputed. The imputation model (linear regression) was done separately for each treatment arm and included baseline value as a covariate and was fitted to all subjects with a measurement regardless of treatment status at week 104.

^3For body weight the ‘change from baseline’ and ‘difference to placebo’ the unit is percentage change from baseline.

^4Baseline value is the geometric mean.

The reduction of MACE with WEGOVY was not impacted by age, sex, race, ethnicity, BMI at baseline, or level of renal function impairment.

14.2 Weight Reduction and Long-term Maintenance Studies in Adults with Obesity or Overweight

Overview of Clinical Studies in Adults
The safety and efficacy of WEGOVY for weight reduction and long-term maintenance of body weight in conjunction with a reduced calorie diet and increased physical activity were studied in three 68-week, randomized, double-blind, placebo-controlled trials; one 68-week, randomized, double-blind, placebo withdrawal trial; and one 68-week, randomized, double-blind trial that investigated 2 different doses of WEGOVY versus placebo. In Studies 2 (NCT#03548935), 3 (NCT#03552757), and 4 (NCT#03611582), WEGOVY or matching placebo was escalated to 2.4 mg subcutaneous weekly during a 16-week period followed by 52 weeks on maintenance dose. In Study 5 (NCT#03548987), WEGOVY was escalated during a 20-week run-in period, and patients who reached a WEGOVY 2.4 mg subcutaneous weekly dosage after the run-in period were randomized to either continued treatment with WEGOVY or placebo for 48 weeks. In Study 6 (NCT#03811574), WEGOVY was escalated to 1.7 mg or 2.4 mg subcutaneous weekly dosages or placebo over 12 to 16 weeks followed by 52 weeks on either maintenance dose.

In Studies 2, 3 and 5, all patients received instruction for a reduced calorie diet (approximately 500 kcal/day deficit) and increased physical activity counseling (recommended to a minimum of 150 min/week) that began with the first dose of study medication or placebo and continued throughout the trial. In Study 4, patients received an initial 8-week low-calorie diet (total energy intake 1,000 to 1,200 kcal/day) followed by 60 weeks of a reduced calorie diet(1200-1800 kcal/day) and increased physical activity (100 mins/week with gradual increase to 200 mins/week).

Study 2 was a 68-week trial that enrolled 1,961 patients with obesity (BMI greater than or equal to 30 kg/m^2) or with overweight (BMI 27-29.9 kg/m^2) and at least one weight-related comorbid condition, such as treated or untreated dyslipidemia or hypertension; patients with type 2 diabetes mellitus were excluded. Patients were randomized in a 2:1 ratio to either WEGOVY or placebo. At baseline, mean age was 46 years (range 18-86), 74% were female, 75% were White, 13% were Asian and 6% were Black or African American. A total of 12% were Hispanic or Latino ethnicity. Mean baseline body weight was 105.3 kg and mean BMI was 37.9 kg/m^2.

Study 3 was a 68-week trial that enrolled 807 patients with type 2 diabetes and BMI greater than or equal to 27 kg/m^2. Patients included in the trial had HbA1c 7-10% and were treated with either: diet and exercise alone or 1 to 3 oral anti‑diabetic drugs (metformin, sulfonylurea, glitazone or sodium-glucose co-transporter 2 inhibitor). Patients were randomized in a 1:1 ratio to receive either WEGOVY or placebo. At baseline, the mean age was 55 years (range 19-84), 51% were female, 62% were White, 26% were Asian and 8% were Black or African American. A total of 13% were Hispanic or Latino ethnicity. Mean baseline body weight was 99.8 kg and mean BMI was 35.7 kg/m^2.

Study 4 was a 68-week trial that enrolled 611 patients with obesity (BMI greater than or equal to 30 kg/m^2) or with overweight (BMI 27-29.9 kg/m^2) and at least one weight-related comorbid condition such as treated or untreated dyslipidemia or hypertension; patients with type 2 diabetes mellitus were excluded. The patients were randomized in a 2:1 ratio to receive either WEGOVY or placebo. At baseline, the mean age was 46 years, 81% were female, 76% were White, 19% were Black or African American and 2% were Asian. A total of 20% were Hispanic or Latino ethnicity. Mean baseline body weight was 105.8 kg and mean BMI was 38.0 kg/m^2.

Study 5 was a 68-week trial that enrolled 902 patients with obesity (BMI greater than or equal to 30 kg/m^2) or with overweight (BMI 27-29.9 kg/m^2) and at least one weight-related comorbid condition such as treated or untreated dyslipidemia or hypertension; patients with type 2 diabetes mellitus were excluded. Mean body weight at baseline for the 902 patients was 106.8 kg and mean BMI was 38.3 kg/m². All patients received WEGOVY during the run-in period of 20 weeks that included 16 weeks of dose escalation. Trial product was permanently discontinued before randomization in 99 of 902 patients (11%); the most common reason was adversereactions (n=48, 5.3%); 803 patients reached WEGOVY 2.4 mg and were then randomized in a 2:1 ratio to either continue on WEGOVY or receive placebo. Among the 803 randomized patients, the mean age was 46 years, 79% were female, 84% were White, 13% were Black or African American, and 2% Asian. A total of 8% were Hispanic or Latino ethnicity. Mean body weight at randomization (week 20) was 96.1 kg and mean BMI at randomization (week 20) was 34.4 kg/m^2.

Study 6 was a 68-week trial that enrolled 401 East-Asian patients (Japan and South Korea) with BMI greater than or equal to 35 kg/m^2 and at least one weight-related comorbid condition or with BMI 27-34.9 kg/m^2 and at least two weight-related comorbid conditions. The patients were randomized 2:1:1 to receive WEGOVY 2.4 mg, WEGOVY 1.7 mg, or placebo. At baseline, the mean age was 51 years, 63% were male, and all patients were Asian. Mean baseline body weight was 87.5 kg and mean BMI was 31.9 kg/m^2. At baseline, 24.7% of patients had type 2 diabetes mellitus.

Results
The proportions of patients who discontinued study drug in Studies 2, 3, and 4 was 16.0% for the WEGOVY-treated group and 19.1% for the placebo-treated group, and 6.8% of patients treated with WEGOVY and 3.2% of patients treated with placebo discontinued treatment due to an adverse reaction [see Adverse Reactions (6.1)]. In Study 5, the proportions of patients who discontinued study drug were 5.8% and 11.6% for WEGOVY and placebo, respectively. In Study 6, the proportions of patients who discontinued study drug were 7.9%, 6.5%, and 3.0% for WEGOVY 1.7 mg, WEGOVY 2.4 mg, and placebo, respectively.

For Studies 2, 3 and 4, the primary efficacy parameters were mean percent change in body weight and the percentages of patients achieving greater than or equal to 5% weight loss from baseline to week 68.

After 68 weeks, treatment with WEGOVY resulted in a statistically significant reduction in body weight compared with placebo. Greater proportions of patients treated with WEGOVY achieved 5%, 10% and 15% weight loss than those treated with placebo as shown in Table 7.

Table 7. Changes in Body Weight at Week 68 in Studies 2, 3, and 4

 | Study 2 (Obesity or overweight with comorbidity) |  | Study 3 (Type 2 diabetes with obesity or overweight) |  | Study 4 (Obesity or overweight with comorbidity undergoing intensive lifestyle therapy)
Intention-to-Treat^1 | PLACEBO N = 655 | WEGOVY N = 1306 | PLACEBO N = 403 | WEGOVY N = 404 | PLACEBO N = 204 | WEGOVY N = 407
Body Weight
Baseline mean (kg) | 105.2 | 105.4 | 100.5 | 99.9 | 103.7 | 106.9
% change from baseline (LSMean) | -2.4 | -14.9 | -3.4 | -9.6 | -5.7 | -16.0
% difference from placebo (LSMean) (95% CI) |  | -12.4 (‑13.3; ‑11.6)* |  | -6.2 (-7.3; -5.2)* |  | -10.3 (-11.8; -8.7)*
% of Patients losing greater than or equal to 5% body weight | 31.1 | 83.5 | 30.2 | 67.4 | 47.8 | 84.8
% difference from placebo (LSMean) (95% CI) |  | 52.4; (48.1; 56.7)* |  | 37.2 (30.7; 43.8)* |  | 37.0 (28.9; 45.2)*
% of Patients losing greater than or equal to 10% body weight | 12.0 | 66.1 | 10.2 | 44.5 | 27.1 | 73.0
% difference from placebo (LSMean) (95% CI) |  | 54.1; (50.4; 57.9)* |  | 34.3 (28.4; 40.2)* |  | 45.9 (38.0; 53.7)*
% of Patients losing greater than or equal to 15% body weight | 4.8 | 47.9 | 4.3 | 25.1 | 13.2 | 53.4
% difference from placebo (LSMean) (95% CI) |  | 43.1; (39.8; 46.3)* |  | 20.7; (15.7; 25.8)* |  | 40.2 (33.1; 47.3)*

LSMean = least squares mean; CI = confidence interval

^1The intent-to-treat population includes all randomized patients. In Study 2, at week 68, the body weight was missing for 7.2% and 11.9% of patients randomized to WEGOVY and placebo, respectively. In Study 3, at week 68, the body weight was missing for 4.0% and 6.7% of patients randomized to WEGOVY and placebo, respectively. In Study 4, at week 68, the body weight was missing for 8.4% and 7.4% of patients randomized to WEGOVY and placebo, respectively. Missing data were imputed from retrieved subjects of the same randomized treatment arm (RD-MI).

* p<0.0001 (unadjusted 2-sided) for superiority.

For Study 5, the primary efficacy parameter was mean percent change in body weight from randomization (week 20) to week 68.

From randomization (week 20) to week 68, treatment with WEGOVY resulted in a statistically significant reduction in body weight compared with placebo (Table 8). Because patients who discontinued WEGOVY during titration and those who did not reach the 2.4 mg weekly dose were not eligible for the randomized treatment period, the results may not reflect the experience of patients in the general population who are first starting WEGOVY.

Table 8. Changes in Body Weight at Week 68 in Study 5 (Obesity or overweight with comorbidity after 20-week run-in)

 | WEGOVY; N = 803^1
Body Weight (only randomized patients)
Mean at week 0 (kg) | 107.2
 | PLACEBO; N = 268 | WEGOVY; N = 535
Body Weight
Mean at week 20 (SD) (kg) | 95.4 (22.7) | 96.5 (22.5)
% change from week 20 at week 68 (LSMean) | 6.9 | -7.9
% difference from placebo (LSMean) (95% CI) |  | -14.8 (-16.0; -13.5)*

LSMean = least squares mean; CI = confidence interval

^1902 patients were enrolled at week 0 with a mean baseline body weight of 106.8 kg. The intent-to-treat population includes all randomized patients. At week 68, the body weight was missing for 2.8% and 6.7% of patients randomized to WEGOVY and placebo, respectively. Missing data were imputed from retrieved subjects of the same randomized treatment arm (RD-MI).

*p<0.001 (unadjusted 2-sided) for superiority, controlled for multiplicity.

For Study 6, the primary efficacy parameters were mean percent change in body weight and the percentage of patients achieving greater than or equal to 5% weight loss from baseline to week 68.

After 68 weeks, treatment with WEGOVY 1.7 mg and 2.4 mg resulted in a statistically significant reduction in body weight compared with placebo. Greater proportions of patients treated with WEGOVY achieved 5%, 10%, and 15% weight loss than those treated with placebo as shown in Table 9.

Table 9. Changes in Body Weight at Week 68 in Study 6 in East-Asian Patients (WEGOVY 1.7 mg)

 | Study 6 (BMI ≥35 kg/m^2 with at least one comorbidity or; BMI 27-34.9 kg/m^2 with at least two comorbidities)
Intention-to-treat^1 | PLACEBO; N = 101 | WEGOVY 1.7 mg; N = 101 | WEGOVY 2.4 mg; N = 199
Body Weight
Baseline mean (kg) | 90.2 | 86.1 | 86.9
% change from baseline (LSMean) | -2.1 | -9.6 | -13.2
% difference from placebo (LSMean) (95% CI) |  | -7.5; (-9.6; -5.4)* | -11.1; (-12.9; -9.2)*
% of Patients losing greater than or equal to 5% body weight | 19.4 | 72.8 | 84.0
% difference from placebo (LSMean) (95% CI) |  | 53.3; (41.0; 65.6)* | 64.5; (54.8; 74.3)*
% of Patients losing greater than or equal to 10% body weight | 4.5 | 39.1 | 59.9
% difference from placebo (LSMean) (95% CI) |  | 34.5; (23.9; 45.1)* | 55.4; (47.3; 63.6)*
% of Patients losing greater than or equal to 15% body weight | 2.6 | 20.8 | 38.2
% difference from placebo (LSMean) (95% CI) |  | 18.2; (9.8; 26.7)* | 35.6; (27.9; 43.3)*

LSMean = least squares mean; CI = confidence interval
^1The intent-to-treat population includes all randomized patients. At baseline, 24.7% of patients had type 2 diabetes mellitus. At week 68, the body weight was missing for 3%, 3%, and 1% of patients randomized to WEGOVY 1.7 mg, WEGOVY 2.4 mg, and placebo, respectively. Missing data were imputed from retrieved subjects of the same randomized treatment arm (RD-MI).

*p<0.0001 (unadjusted 2-sided) for superiority.

A reduction in body weight was observed with WEGOVY irrespective of age, sex, race, ethnicity, BMI at baseline, body weight (kg) at baseline, and level of renal function impairment.

The cumulative frequency distributions of change in body weight are shown in Figure 5 and Figure 6 for Studies 2 and 3. One way to interpret this figure is to select a change in body weight of interest on the horizontal axis and note the corresponding proportions of patients (vertical axis) in each treatment group who achieved at least that degree of weight loss. For example, note that the vertical line arising from ‑10% in Study 2 intersects the WEGOVY and placebo curves at approximately 66%, and 12%, respectively, which correspond to the values shown in Table 7.

Figure 5. Change in body weight (%) from baseline to week 68 (Study 2)

Observed data from in-trial period including imputed data for missing observations (RD-MI).

Figure 6. Change in body weight (%) from baseline to week 68 (Study 3)

Observed data from in-trial period including imputed data for missing observations (RD-MI).

The time courses of weight loss with WEGOVY and placebo from baseline through week 68 are depicted in Figure 7, Figure 8 and Figure 9.

Figure 7. Change from baseline (%) in body weight (Study 2 on left and Study 3 on right)

Observed values for patients completing each scheduled visit, and estimates with multiple imputations from retrieved dropouts (RD-MI)

Figure 8 Change from baseline (%) in body weight (Study 4 on left and Study 5a on right)

Observed values for patients completing each scheduled visit, and estimates with multiple imputations from retrieved dropouts (RD-MI)
aChange from week 0 was not a primary endpoint in study 5. Dotted line indicates time of randomization. Randomized patients (shown) do not include 99 patients that discontinued during the 20-week run-in period.

Figure 9. Change in body weight (%) from baseline to week 68 (Study 6 in East-Asian Patients)

Observed values for patients completing each scheduled visit and estimates with multiple imputations from retrieved dropouts (RD-MI). At baseline, 24.7% of patients had type 2 diabetes mellitus.

Effect of WEGOVY on Anthropometry and Cardiometabolic Parameters in Adults

Changes in waist circumference and cardiometabolic parameters with WEGOVY are shown in Table 10 for Studies 2, 3, and 4; in Table 11 for Study 5; and in Table 12 for Study 6.

Table 10. Changes in Anthropometry and Cardiometabolic Parameters at Week 68 in Studies 2, 3, and 4

 | Study 2 (Obesity or overweight with comorbidity) |  | Study 3 (Type 2 diabetes with obesity or overweight) |  | Study 4 (Obesity or overweight with comorbidity undergoing intensive lifestyle therapy)
Intention-to-Treat | PLACEBO N = 655 | WEGOVY N = 1306 | PLACEBO N = 403 | WEGOVY N = 404 | PLACEBO N = 204 | WEGOVY N = 407
Waist Circumference (cm); Baseline Changes from baseline (LSMean^1) Difference from placebo (LSMean) | 114.8; -4.1 | 114.6; -13.5; -9.4 | 115.5; -4.5 | 114.5; -9.4; -4.9 | 111.8; -6.3 | 113.6; -14.6; -8.3
Systolic Blood Pressure (mmHg); Baseline Changes from baseline (LSMean^1) Difference from placebo (LSMean) | 127; -1.1 | 126; -6.2; -5.1 | 130; -0.5 | 130; -3.9; -3.4 | 124; -1.6 | 124; -5.6; -3.9
Diastolic Blood Pressure (mmHg)^2; Baseline Changes from baseline (LSMean^1) Difference from placebo (LSMean) | 80; -0.4 | 80; -2.8; -2.4 | 80; -0.9 | 80; -1.6; -0.7 | 81; -0.8 | 80; -3.0; -2.2
Heart Rate^2,3; Baseline Changes from baseline (LSMean) Difference from placebo (LSMean) | 72; -0.7 | 72; 3.5; 4.3 | 76; -0.2 | 75; 2.5; 2.7 | 71; 2.1 | 71; 3.1; 1.0
HbA1c (%)^2; Baseline Changes from baseline (LSMean^1) Difference from placebo (LSMean) | 5.7; -0.2 | 5.7; -0.4; -0.3 | 8.1; -0.4 | 8.1; -1.6; -1.2 | 5.8; -0.3 | 5.7; -0.5; -0.2
Total Cholesterol (mg/dL)^2,4; Baseline Percent Change from baseline (LSMean^1) Relative difference from placebo (LSMean) | 192.1; 0.1 | 189.6; -3.3; -3.3 | 170.8; -0.5 | 170.8; -1.4; -0.9 | 188.7; 2.1 | 185.4; -3.9; -5.8
LDL Cholesterol (mg/dL)^2,4; Baseline Percent Change from baseline (LSMean^1) Relative difference from placebo (LSMean) | 112.5; 1.3 | 110.3; -2.5; -3.8 | 90.1; 0.1 | 90.1; 0.5; 0.4 | 111.8; 2.6 | 107.7; -4.7; -7.1
HDL (mg/dL)^2,4; Baseline Percent Change from baseline (LSMean^1) Relative difference from placebo (LSMean) | 49.5; 1.4 | 49.4; 5.2; 3.8 | 43.8; 4.1 | 44.7; 6.9; 2.7 | 50.9; 5.0 | 51.6; 6.5; 1.5
Triglycerides (mg/dL)^2,4; Baseline Percent Change from baseline (LSMean^1) Relative difference from placebo (LSMean) | 127.9; -7.3 | 126.2; -21.9; -15.8 | 159.5; -9.4 | 154.9; -22.0; -13.9 | 110.9; -6.5 | 107.9; -22.5; -17.0

Missing data were imputed from retrieved subjects of the same randomized treatment arm (RD-MI)

^1Model based estimates based on an analysis of covariance model including treatment (and stratification factors for Study 3 only) as a factor and baseline value as a covariate

^2Not included in the pre-specified hierarchical testing (except HbA1c for Study 3)

^3Model based estimates based on a mixed model for repeated measures including treatment (and stratification factors for Study 3 only) as a factor and baseline values as a covariate

^4Baseline value is the geometric mean

Table 11. Mean Changes in Anthropometry and Cardiometabolic Parameters in Study 5 (Obesity or overweight with comorbidity after 20-week run-in)^1

 | PLACEBO; N = 268 |  | WEGOVY; N = 535
 | Randomization; (week 20) | Change from Randomization (week 20) to week 68; (LSMean^1) | Randomization; (week 20) | Change from Randomization (week 20) to week 68; (LSMean^1) | Difference from placebo; (LSMean)
Waist Circumference (cm) | 104.7 | 3.3 | 105.5 | -6.4 | -9.7
Systolic Blood Pressure (mmHg) | 121 | 4.4 | 121 | 0.5 | -3.9
Diastolic Blood Pressure (mmHg)^2 | 78 | 0.9 | 78 | 0.3 | -0.5
Heart Rate^2,3 | 76 | -5.3 | 76 | -2.0 | 3.3
HbA1c (%)^2 | 5.4 | 0.1 | 5.4 | -0.1 | -0.2
 | Randomization; (week 20) | % Change from Randomization; (week 20); (LSMean^1) | Randomization; (week 20) | % Change from Randomization; (week 20); (LSMean^1) | Relative difference from placebo (LSMean)
Total Cholesterol (mg/dL)^2,4 | 175.1 | 11.4 | 175.9 | 4.9 | -5.8
LDL Cholesterol (mg/dL)^2,4 | 109.1 | 7.6 | 108.7 | 1.1 | -6.1
HDL Cholesterol (mg/dL)^2,4 | 43.6 | 17.8 | 44.5 | 18.2 | 0.3
Triglycerides (mg/dL)^2,4 | 95.3 | 14.8 | 98.1 | -5.6 | -17.8

Missing data were imputed from retrieved subjects of the same randomized treatment arm (RD-MI)

^1Model based estimates based on an analysis of covariance model including treatment as a factor and baseline value as a covariate

^2Not included in the pre-specified hierarchical testing

^3Model based estimates based on a mixed model for repeated measures including treatment as a factor and baseline values as a covariate

^4Baseline value is the geometric mean

Table 12. Mean Changes in Anthropometry and Cardiometabolic Parameters at Week 68 in Study 6 in East-Asian Patients (WEGOVY 1.7 mg)

 | Study 6 (BMI ≥35 kg/m^2 with at least one comorbidity or BMI 27-34.9 kg/m^2 with at least two comorbidities)
Intention-to-treat | PLACEBO; N = 101 | WEGOVY 1.7 mg; N = 101 | WEGOVY 2.4 mg; N = 199
Waist circumference (cm); Baseline; Change from baseline (LSMean^1); Difference from placebo (LSMean) | 103.8; -1.8 | 101.4; -7.7; -5.9 | 103.8; -11.0; -9.3
Systolic blood pressure (mmHg)^2; Baseline; Change from baseline (LSMean^1); Difference from placebo (LSMean) | 133; -5.3 | 135; -10.8; -5.4 | 133; -10.8; -5.5
Diastolic blood pressure (mmHg)^2; Baseline; Change from baseline (LSMean^1); Difference from placebo (LSMean) | 86; -2.2 | 85; -4.6; -2.4 | 83; -5.3; -3.1
Heart Rate^(2, 3); Baseline; Change from baseline (LSMean); Difference from placebo (LSMean) | 73; 2.4 | 73; 4.4; 2.0 | 73; 6.3; 3.9
HbA1c (%)^2; Baseline; Change from baseline (LSMean^1); Difference from placebo (LSMean) | 6.4; 0.0 | 6.4; -0.9; -0.9 | 6.4; -0.9; -0.9
Total Cholesterol (mg/dL)^2,4; Baseline; Percent change from baseline (LSMean^1); Relative difference from placebo (LSMean) | 203.1; 0.8 | 203.3; -6.6; -7.3 | 197.2; -8.7; -9.4
LDL Cholesterol (mg/dL)^2,4; Baseline; Percent change from baseline (LSMean^1); Relative difference from placebo (LSMean) | 123.3; -3.8 | 120.1; -10.1; -6.5 | 116.5; -14.6; -11.2
HDL Cholesterol (mg/dL)^2,4; Baseline; Percent change from baseline (LSMean^1); Relative difference from placebo (LSMean) | 48.7; 5.9 | 50.2; 6.7; 0.7 | 50.8; 9.2; 3.1
Triglyceride (mg/dL)^2,4; Baseline; Percent change from baseline (LSMean^1); Relative difference from placebo (LSMean) | 134.2; 5.5 | 138.8; -19.5; -23.7 | 127.1; -21.2; -25.3

Missing data were imputed from retrieved subjects of the same randomized treatment arm (RD-MI). At baseline, 24.7% of patients had type 2 diabetes mellitus.

^1Model based estimates based on an analysis of covariance model including treatment and type 2 diabetes status as factors and baseline value as a covariate

^2Not included in the pre-specified hierarchical testing

^3Model based estimates based on a mixed model for repeated measures including treatment and type 2 diabetes status as factors and baseline values as a covariate

^4Baseline value is the geometric mean

14.3 Weight Reduction and Long-Term Maintenance Study in Pediatric Patients Aged 12 Years and Older with Obesity

Overview of Clinical Trial in Pediatric Patients
WEGOVY was evaluated in a 68-week, double-blind, randomized, parallel group, placebo-controlled, multi-center trial in 201 pubertal pediatric patients aged 12 years and older with BMI corresponding to ≥95th percentile standardized for age and sex (Study 7) (NCT#04102189). After a 12-week lifestyle run-in period (including dietary recommendations and physical activity counseling), patients were randomized 2:1 to WEGOVY once weekly or placebo once weekly. WEGOVY or matching placebo was escalated to 2.4 mg or maximally tolerated dose during a 16-week period followed by 52 weeks on maintenance dose. Of WEGOVY-treated patients who completed the trial, 86.7% were on the 2.4 mg dose at the end of the trial; for 5% of patients, 1.7 mg was the maximum tolerated dose.

The mean age was 15 years; 38% of patients were male; 79% were White, 8% were Black or African American, 2% were Asian, and 11% were of other or unknown race; and 11% were of Hispanic or Latino ethnicity. The mean baseline body weight was 108 kg, and mean BMI was 37 kg/m^2.

Results

The proportions of patients who discontinued study drug were 10% for the WEGOVY-treated group and 10% for the placebo-treated group.

The primary endpoint was percent change in BMI from baseline to week 68. After 68 weeks, treatment with WEGOVY resulted in a statistically significant reduction in percent BMI compared with placebo. Greater proportions of patients treated with WEGOVY achieved ≥5% reduction in baseline BMI than those treated with placebo as shown in Table 13.

Table 13. Changes in Weight and BMI at Week 68 in Pediatric Patients with Obesity Aged 12 Years and Older in Study 7

Intention-to-Treata | PLACEBO N = 67 | WEGOVY N = 134
BMI
Baseline mean (kg/m^2) | 35.7 | 37.7
% change from baseline in BMI (LSMean) | 0.6 | -16.1
% difference from placebo (LSMean) (95% CI) |  | -16.7; (-20.3; -13.2)*
% of Patients with greater than or equal to 5% reduction in baseline BMIb | 19.7 | 77.1
% difference from placebo (LSMean) |  | 57.4
% of Patients with greater than or equal to 10% reduction in baseline BMIb | 7.7 | 65.1
% difference from placebo (LSMean) |  | 57.5
% of Patients with greater than or equal to 15% reduction in baseline BMIb | 4.0 | 57.8
% difference from placebo (LSMean) |  | 53.9
Body Weightb
Baseline mean (kg) | 102.6 | 109.9
% change from baseline (LSMean)a | 2.7 | -14.7
% difference from placebo (LSMean) |  | -17.4

LSMean = least squares mean; CI = confidence interval

aThe intention-to-treat population includes all randomized patients. Missing data were imputed using available data according to value and timing of last available observation on treatment and endpoint’s baseline value from retrieved subjects (RD-MI). At week 68, the BMI was missing for 2.2% and 7.5% of patients randomized to WEGOVY and placebo, respectively.

bParameters not included in the pre-specified hierarchical testing.

* p<0.0001 (unadjusted 2-sided) for superiority.

The time course of change in BMI with WEGOVY and placebo from baseline through week 68 is depicted in Figure 10. The cumulative frequency distribution of change in BMI is shown in Figure 11.

Figure 10. Change from Baseline (%) in BMI in Pediatric Patients with Obesity Aged 12 Years and Older in Study 7

Observed values for patients completing each scheduled visit, and estimates with multiple imputations from retrieved dropouts (RD-MI)

Figure 11. Change in BMI (%) from Baseline to Week 68 in Pediatric Patients with Obesity Aged 12 Years and Older in Study 7

Observed data from in-trial period including imputed data for missing observations (RD-MI)

Effect of WEGOVY on Anthropometry and Cardiometabolic Parameters in Pediatric Patients with Obesity Aged 12 Years and Older

Changes in waist circumference and cardiometabolic parameters with WEGOVY are shown in Table 14 for the study in pediatric patients aged 12 years and older.

Table 14. Mean Changes in Anthropometry and Cardiometabolic Parameters in Pediatric Patients with Obesity Aged 12 Years and Older in Study 7^1

 | PLACEBO; N = 67 |  | WEGOVY; N = 134
 | Baseline | Change from Baseline; (LSMean) | Baseline | Change from Baseline; (LSMean) | Difference from placebo; (LSMean)
Waist Circumference (cm)^2 | 107.3 | -0.6 | 111.9 | -12.7 | -12.1
Systolic Blood Pressure (mmHg)^2 | 120 | -0.8 | 120 | -2.7 | -1.9
Diastolic Blood Pressure (mmHg)^2 | 73 | -0.8 | 73 | -1.4 | -0.6
Heart Rate^3 | 76 | -2.3 | 79 | 1.2 | 3.5
HbA1c (%)^2,4 | 5.4 | -0.1 | 5.5 | -0.4 | -0.2
 | Baseline | % Change from Baseline; (LSMean) | Baseline | % Change from Baseline; (LSMean) | Relative difference from placebo (LSMean)
Total Cholesterol (mg/dL)^2,5 | 160.1 | -1.3 | 159.4 | -8.3 | -7.1
LDL Cholesterol (mg/dL)^2,5 | 91.7 | -3.6 | 89.8 | -9.9 | -6.6
HDL Cholesterol (mg/dL)^2,5 | 43.3 | 3.2 | 43.7 | 8.0 | 4.7
Triglycerides (mg/dL)^2,5 | 108.0 | 2.6 | 111.3 | -28.4 | -30.2

^1Parameters listed in the table were not included in the pre-specified hierarchical testing.

^2Missing data were imputed using available data according to value and timing of last available observation on treatment and endpoint’s baseline value from retrieved subjects (RD-MI). Model based estimates based on an analysis of covariance model including treatment and stratification groups (gender, Tanner stage group) and the interaction between stratification groups as factors and baseline value as a covariate.

^3Model based estimates based on a mixed model for repeated measures including treatment as a factor and baseline value as a covariate all nested within visit.

^4For patients without type 2 diabetes at randomization (N=129 for WEGOVY-treated patients and N=64 for placebo-treated patients).

^5Baseline value is the geometric mean.

16 HOW SUPPLIED/STORAGE AND HANDLING

Product: 50090-5824

NDC: 50090-5824-0 .5 mL in a SYRINGE, PLASTIC / 4 in a CARTON

17 PATIENT COUNSELING INFORMATION

Advise the patient to read the FDA-approved patient labeling (Medication Guide and Instructions for Use).

Risk of Thyroid C-cell Tumors

Inform patients that semaglutide causes thyroid C-cell tumors in rodents and that the human relevance of this finding has not been determined. Counsel patients to report symptoms of thyroid tumors (e.g., a lump in the neck, hoarseness, dysphagia, or dyspnea) to their physician [see Boxed Warning and Warnings and Precautions (5.1)].

Acute Pancreatitis

Inform patients of the potential risk for acute pancreatitis. Instruct patients to discontinue WEGOVY promptly and contact their physician if pancreatitis is suspected (severe abdominal pain that may radiate to the back, and which may or may not be accompanied by vomiting) [see Warnings and Precautions (5.2)].

Acute Gallbladder Disease

Inform patients of the risk of acute gallbladder disease. Advise patients that substantial or rapid weight loss can increase the risk of gallbladder disease, but that gallbladder disease may also occur in the absence of substantial or rapid weight loss. Instruct patients to contact their healthcare provider for appropriate clinical follow-up if gallbladder disease is suspected [see Warnings and Precautions (5.3)].

Hypoglycemia

Inform patients of the risk of hypoglycemia and educate patients on the signs and symptoms of hypoglycemia. Advise patients with diabetes mellitus on glycemic lowering therapy that they may have an increased risk of hypoglycemia when using WEGOVY and to report signs and/or symptoms of hypoglycemia to their healthcare provider [see Warnings and Precautions (5.4)].

Dehydration and Renal Impairment

Advise patients treated with WEGOVY of the potential risk of dehydration due to gastrointestinal adverse reactions and take precautions to avoid fluid depletion. Inform patients of the potential risk for worsening renal function and explain the associated signs and symptoms of renal impairment, as well as the possibility of dialysis as a medical intervention if renal failure occurs [see Warnings and Precautions (5.5)].

Hypersensitivity Reactions

Inform patients that serious hypersensitivity reactions have been reported during postmarketing use of semaglutide, the active ingredient in WEGOVY. Advise patients on the symptoms of hypersensitivity reactions and instruct them to stop taking WEGOVY and seek medical advice promptly if such symptoms occur [see Warnings and Precautions (5.6)].

Diabetic Retinopathy Complications in Patients with Type 2 Diabetes

Inform patients with type 2 diabetes to contact their physician if changes in vision are experienced during treatment with WEGOVY [see Warnings and Precautions (5.7)].

Heart Rate Increase

Instruct patients to inform their healthcare providers of palpitations or feelings of a racing heartbeat while at rest during WEGOVY treatment [see Warnings and Precautions (5.8)].

Suicidal Behavior and Ideation

Advise patients to report emergence or worsening of depression, suicidal thoughts or behavior, and/or any unusual changes in mood or behavior. Inform patients that if they experience suicidal thoughts or behaviors, they should stop taking WEGOVY [see Warnings and Precautions (5.9)].

Pregnancy

WEGOVY may cause fetal harm. Advise patients to inform their healthcare provider of a known or suspected pregnancy. Advise patients who are exposed to WEGOVY during pregnancy to contact Novo Nordisk at 1-877-390-2760 or www.wegovypregnancyregistry.com [see Use in Specific Populations (8.1)].

Manufactured by:

Novo Nordisk A/S

DK-2880 Bagsvaerd

Denmark

For additional information about WEGOVY contact:

Novo Nordisk Inc.

800 Scudders Mill Road

Plainsboro, NJ 08536

1-833-934-6891

Version: 4

WEGOVY® is a registered trademark of Novo Nordisk A/S.

PATENT INFORMATION: http://www.novonordisk-us.com/products/product-patents.html

© 2024 Novo Nordisk

Medication Guide

WEGOVY® (wee-GOH-vee)

(semaglutide) injection, for subcutaneous use

Read this Medication Guide and Instructions for Use before you start using WEGOVY and each time you get a refill. There may be new information. This information does not take the place of talking to your healthcare provider about your medical condition or your treatment.

What is the most important information I should know about WEGOVY?

WEGOVY may cause serious side effects, including:

- Possible thyroid tumors, including cancer. Tell your healthcare provider if you get a lump or swelling in your neck, hoarseness, trouble swallowing, or shortness of breath. These may be symptoms of thyroid cancer. In studies with rodents, WEGOVY and medicines that work like WEGOVY caused thyroid tumors, including thyroid cancer. It is not known if WEGOVY will cause thyroid tumors or a type of thyroid cancer called medullary thyroid carcinoma (MTC) in people.
- Do not use WEGOVY if you or any of your family have ever had a type of thyroid cancer called medullary thyroid carcinoma (MTC), or if you have an endocrine system condition called Multiple Endocrine Neoplasia syndrome type 2 (MEN 2).

What is WEGOVY?

- WEGOVY is an injectable prescription medicine used with a reduced calorie diet and increased physical activity:
- to reduce the risk of major cardiovascular events such as death, heart attack, or stroke in adults with known heart disease and with either obesity or overweight.
- that may help adults and children aged 12 years and older with obesity, or some adults with overweight who also have weight-related medical problems, to help them lose excess body weight and keep the weight off.
- WEGOVY contains semaglutide and should not be used with other semaglutide-containing products or other GLP-1 receptor agonist medicines.
- It is not known if WEGOVY is safe and effective for use in children under 12 years of age.

Do not use WEGOVY if:

- you or any of your family have ever had a type of thyroid cancer called medullary thyroid carcinoma (MTC) or if you have an endocrine system condition called Multiple Endocrine Neoplasia syndrome type 2 (MEN 2).
- you have had a serious allergic reaction to semaglutide or any of the ingredients in WEGOVY. See the end of this Medication Guide for a complete list of ingredients in WEGOVY. Symptoms of a serious allergic reaction include:

- swelling of your face, lips, tongue or throat

- fainting or feeling dizzy

- problems breathing or swallowing

- very rapid heartbeat

- severe rash or itching

Before using WEGOVY, tell your healthcare provider if you have any other medical conditions, including if you:

- have or have had problems with your pancreas or kidneys.
- have type 2 diabetes and a history of diabetic retinopathy.
- have or have had depression or suicidal thoughts, or mental health issues.
- are pregnant or plan to become pregnant. WEGOVY may harm your unborn baby. You should stop using WEGOVY 2 months before you plan to become pregnant.
  - Pregnancy Exposure Registry: There is a pregnancy exposure registry for women who use WEGOVY during pregnancy. The purpose of this registry is to collect information about the health of you and your baby. Talk to your healthcare provider about how you can take part in this registry or you may contact Novo Nordisk at 1-877-390-2760.
- are breastfeeding or plan to breastfeed. It is not known if WEGOVY passes into your breast milk. You should talk with your healthcare provider about the best way to feed your baby while using WEGOVY.
Tell your healthcare provider about all the medicines you take, including prescription and over-the-counter medicines, vitamins, and herbal supplements. WEGOVY may affect the way some medicines work and some medicines may affect the way WEGOVY works. Tell your healthcare provider if you are taking other medicines to treat diabetes, including sulfonylureas or insulin. WEGOVY slows stomach emptying and can affect medicines that need to pass through the stomach quickly.

Know the medicines you take. Keep a list of them to show your healthcare provider and pharmacist when you get a new medicine.

How should I use WEGOVY?

- Read the Instructions for Use that comes with WEGOVY.
- Use WEGOVY exactly as your healthcare provider tells you to.
- Your healthcare provider should show you how to use WEGOVY before you use it for the first time.
- WEGOVY is injected under the skin (subcutaneously) of your stomach (abdomen), thigh, or upper arm. Do not inject WEGOVY into a muscle (intramuscularly) or vein (intravenously).
- Change (rotate) your injection site with each injection. Do not use the same site for each injection.
- Use WEGOVY 1 time each week, on the same day each week, at any time of the day.
- Start WEGOVY with 0.25 mg per week in your first month. In your second month, increase your weekly dose to 0.5 mg. In the third month, increase your weekly dose to 1 mg. In the fourth month, increase your weekly dose to 1.7 mg. In the fifth month onwards, your healthcare provider may either maintain your dose at 1.7 mg weekly or increase your weekly dose to 2.4 mg.
- If you need to change the day of the week, you may do so as long as your last dose of WEGOVY was given 2 or more days before.
- If you miss a dose of WEGOVY and the next scheduled dose is more than 2 days away (48 hours), take the missed dose as soon as possible. If you miss a dose of WEGOVY and the next schedule dose is less than 2 days away (48 hours), do not administer the dose. Take your next dose on the regularly scheduled day.
- If you miss doses of WEGOVY for more than 2 weeks, take your next dose on the regularly scheduled day or call your healthcare provider to talk about how to restart your treatment.
- You can take WEGOVY with or without food.
- If you take too much WEGOVY, you may have severe nausea, severe vomiting and severe low blood sugar. Call your healthcare provider or go to the nearest hospital emergency room right away if you experience any of these symptoms.

What are the possible side effects of WEGOVY?

WEGOVY may cause serious side effects, including:

- See “What is the most important information I should know about WEGOVY?”
- inflammation of your pancreas (pancreatitis). Stop using WEGOVY and call your healthcare provider right away if you have severe pain in your stomach area (abdomen) that will not go away, with or without vomiting. You may feel the pain from your abdomen to your back.
- gallbladder problems. WEGOVY may cause gallbladder problems including gallstones. Some gallbladder problems need surgery. Call your healthcare provider if you have any of the following symptoms:

- pain in your upper stomach (abdomen)

- yellowing of skin or eyes (jaundice)

- fever

- clay-colored stools

- increased risk of low blood sugar (hypoglycemia), especially those who also take medicines to treat diabetes mellitus such as insulin or sulfonylureas. Low blood sugar in patients with diabetes who receive WEGOVY can be a serious side effect. Talk to your healthcare provider about how to recognize and treat low blood sugar. You should check your blood sugar before you start taking WEGOVY and while you take WEGOVY. Signs and symptoms of low blood sugar may include:

- dizziness or light-headedness

- sweating

- shakiness

- blurred vision

- slurred speech

- weakness

- anxiety

- hunger

- headache

- irritability or mood changes

- confusion or drowsiness

- fast heartbeat

- feeling jitteryt

- kidney problems (kidney failure). In people who have kidney problems, diarrhea, nausea, and vomiting may cause a loss of fluids (dehydration) which may cause kidney problems to get worse. It is important for you to drink fluids to help reduce your chance of dehydration.
- seriousallergic reactions. Stop using WEGOVY and get medical help right away, if you have any symptoms of a serious allergic reaction including:

- swelling of your face, lips, tongue or throat

- severe rash or itching

- very rapid heartbeat

- problems breathing or swallowing

- fainting or feeling dizzy

- change in vision in people with type 2 diabetes. Tell your healthcare provider if you have changes in vision during treatment with WEGOVY.
- increased heart rate. WEGOVY can increase your heart rate while you are at rest. Your healthcare provider should check your heart rate while you take WEGOVY. Tell your healthcare provider if you feel your heart racing or pounding in your chest and it lasts for several minutes.
- depression or thoughts of suicide. You should pay attention to any mental changes, especially sudden changes in your mood, behaviors, thoughts, or feelings. Call your healthcare provider right away if you have any mental changes that are new, worse, or worry you.

The most common side effects of WEGOVY in adults or children aged 12 years and older may include:

- nausea

- stomach (abdomen) pain

- dizziness

- gas

- diarrhea

- headache

- feeling bloated

- stomach flu

- vomiting

- tiredness (fatigue)

- belching

- heartburn

- constipation

- upset stomach

- low blood sugar in people with type 2 diabetes

- runny nose or sore throat

Talk to your healthcare provider about any side effect that bothers you or does not go away. These are not all the possible side effects of WEGOVY.

Call your doctor for medical advice about side effects. You may report side effects to FDA at 1‑800‑FDA‑1088.

General information about the safe and effective use of WEGOVY.

Medicines are sometimes prescribed for purposes other than those listed in a Medication Guide. Do not use WEGOVY for a condition for which it was not prescribed. Do not give WEGOVY to other people, even if they have the same symptoms that you have. It may harm them. You can ask your pharmacist or healthcare provider for information about WEGOVY that is written for health professionals.

What are the ingredients in WEGOVY?

Active Ingredient: semaglutide

Inactive Ingredients: disodium phosphate dihydrate, 1.42 mg; sodium chloride, 8.25 mg; water for injection; and hydrochloric acid or sodium hydroxide may be added to adjust pH.

Manufactured by: Novo Nordisk A/S, DK-2880 Bagsvaerd, Denmark

WEGOVY® is a registered trademark of Novo Nordisk A/S.

PATENT Information: http://novonordisk-us.com/products/product-patents.html

© 2024 Novo Nordisk

For more information, go to startWegovy.com or call 1-833-Wegovy-1.

This Medication Guide has been approved by the U.S. Food and Drug Administration. Revised 03/2024

Instructions for Use

WEGOVY®

(semaglutide) injection

WEGOVY comes in five strengths:

Before you use your WEGOVY pen for the first time, talk to your healthcare provider or your caregiver about how to prepare and inject WEGOVY correctly.

Important information

Read this Instructions for Use before you start using WEGOVY. This information does not replace talking to your healthcare provider about your medical condition or treatment.

· Your WEGOVY pen is for 1 time use only. The WEGOVY pen is for subcutaneous (under the skin) use only.

· The dose of WEGOVY is already set on your pen.

· The needle is covered by the needle cover and the needle will not be seen.

· Do not remove the pen cap until you are ready to inject.

· Do not touch or push on the needle cover. You could get a needle stick injury.

· Your WEGOVY injection will start when the needle cover is pressed firmly against your skin.

· Do not remove the pen from your skin before the yellow bar in the pen window has stopped moving. The medicine may appear on the skin or squirt from the needle and you may not get your full dose of WEGOVY if:

- the pen is removed too early or
- you have not pressed the pen firmly against the skin for the entire injection.

· If the yellow bar does not start moving or stops during the injection, contact your healthcare provider or Novo Nordisk at startWegovy.com or call Novo Nordisk Inc. at 1-833-934-6891.

· The needle cover will lock when the pen is removed from your skin. You cannot stop the injection and restart it later.

· People who are blind or have vision problems should not use the WEGOVY pen without help from a person trained to use the WEGOVY pen.

How do I store WEGOVY?

· Store the WEGOVY pen in the refrigerator between 36°F to 46°F (2°C to 8°C).

· If needed, before removing the pen cap, WEGOVY can be stored from 46°F to 86°F (8°C to 30°C) in the original carton for up to 28 days.

· Keep WEGOVY in the original carton to protect it from light.

· Do not freeze.

· Throw away the pen if WEGOVY has been frozen, has been exposed to light or temperatures above 86°F (30°C), or has been out of the refrigerator for 28 days or longer.

Keep WEGOVY and all medicines out of the reach of children.

How to use your WEGOVY pen

Do not use your WEGOVY pen without receiving training from your healthcare provider. Make sure that you or your caregiver know how to give an injection with the pen before you start your treatment.

Read and follow the instructions so that you use your WEGOVY pen correctly:

Preparation

Step 1. Prepare for your injection.

- Supplies you will need to give your WEGOVY injection:
  - WEGOVY pen
  - 1 alcohol swab or soap and water
  - 1 gauze pad or cotton ball
  - 1 sharps disposable container for used WEGOVY pens

- Wash your hands.
- Check your WEGOVY pen.
  Do not use your WEGOVY pen if:
- The pen appears to have been used or any part of the pen appears broken, for example if it has been dropped.
- The WEGOVY medicine is not clear and colorless through the pen window.
- The expiration date (EXP) has passed.

Contact Novo Nordisk at 1-833-934-6891 if your WEGOVY pen fails any of these checks.

Step 2. Choose your injection site.

• Your healthcare provider can help you choose the injection site that is best for you

- You may inject into your upper leg (front of the thighs), lower stomach (keep 2 inches away from your belly button) or upper arm.

• Do not inject into an area where the skin is tender, bruised, red, or hard. Avoid injecting into areas with scars or stretch marks.

• You may inject in the same body area each week, but make sure it is not in the same spot each time.

Clean the injection site with an alcohol swab or soap and water. Do not touch the injection site after cleaning. Allow the skin to dry before injecting.

Injection

Step 3. Remove pen cap.

• Pull the pen cap straight off your pen.

Step 4. Inject WEGOVY.

• Push the pen firmly against your skin and keep applying pressure until the yellow bar

has stopped moving.

If the yellow bar does not start moving, press the pen more firmly against your skin.

- You will hear 2 clicks during the injection.
- Click 1: the injection has started.
- Click 2: the injection is ongoing.
- If you have problems with the injection, refer to the “Troubleshooting” section.

Throw away pen

Step 5. Throw away (dispose of) pen.

Safely dispose of the WEGOVY pen right away after each use. See “How do I throw away (dispose of) WEGOVY pens?”

• What if blood appears after injection?

If blood appears at the injection site, press the site lightly with a gauze pad or cotton ball.

- If you have problems injecting, change to a more firm injection site, such as upper leg, or upper arm or consider standing up while injecting into the lower stomach.
- If medicine appears on the skin or squirts from the needle, make sure the next time you inject to keep applying pressure until the yellow bar has stopped moving. Then you can lift the pen slowly from your skin.

How do I throw away (dispose of) WEGOVY pens?

Put the used WEGOVY pen in an FDA-cleared sharps disposal container right away after use. Do not throw away (dispose of) the pen in your household trash.

If you do not have an FDA-cleared sharps disposal container, you may use a household container that is:

· made of a heavy-duty plastic,
· able to be closed with a tight-fitting, puncture-resistant lid, without sharps being able to come out,
· upright and stable during use,
· leak-resistant, and
· properly labeled to warn of hazardous waste inside the container.

When your sharps disposal container is almost full, you will need to follow your community guidelines for the right way to dispose of your sharps disposal container. There may be state or local laws about how you should throw away used needles and syringes. For more information about safe sharps disposal, and for specific sharps disposal in the state that you live in, go to the FDA’s website at http://www.fda.gov/safesharpsdisposal.

· Do not reuse the pen.
· Do not recycle the pen or sharps disposal container, or throw them into household trash.

Important: Keep your WEGOVY pen, sharps disposal container and all medicines out of the reach of children.

How do I care for my pen?

Protect your pen

· Do not drop your pen or knock it against hard surfaces.
· Do not expose your pen to any liquids.
· If you think that your pen may be damaged, do not try to fix it. Use a new one.
· Keep the pen cap on until you are ready to inject. Your pen will no longer be sterile if you store an unused pen without the cap, if you pull the pen cap off and put it on again, or if the pen cap is missing. This could lead to an infection.
If you have any questions about WEGOVY, go to startWegovy.com or call Novo Nordisk Inc. at 1-833-Wegovy-1

Manufactured by:

Novo Nordisk A/S

Novo Allé

DK-2880 Bagsvaerd, Denmark

For information about WEGOVY, go to

startWegovy.com or contact:

Novo Nordisk Inc.

800 Scudders Mill Road

Plainsboro, NJ 08536

1-833-Wegovy-1

Version: 2

WEGOVY® is a registered trademark of Novo Nordisk A/S.

PATENT Information: http://novonordisk-us.com/products/product-patents.html

© 2022 Novo Nordisk

This Instructions for Use has been approved by the U.S. Food and Drug Administration.

Revised: August 2022